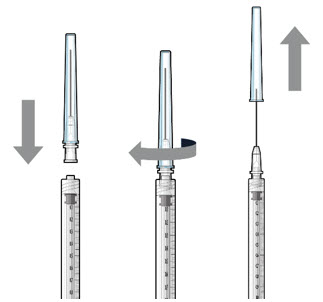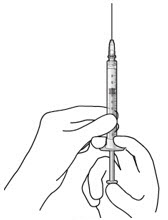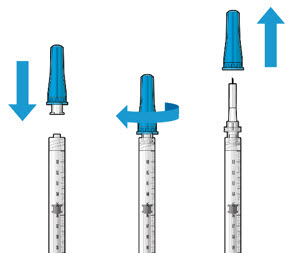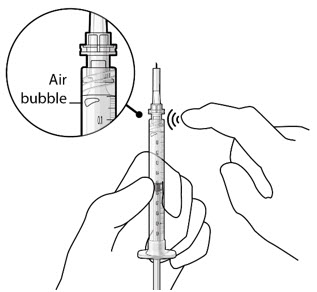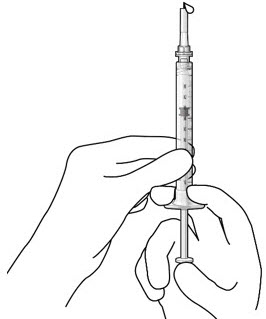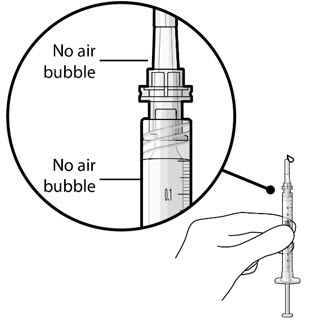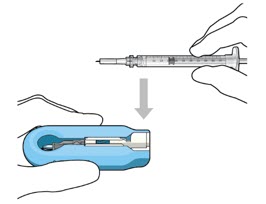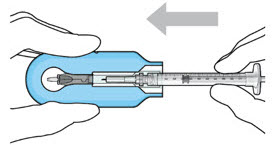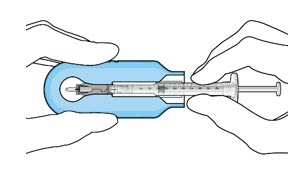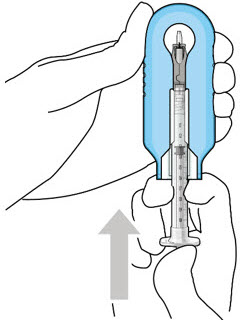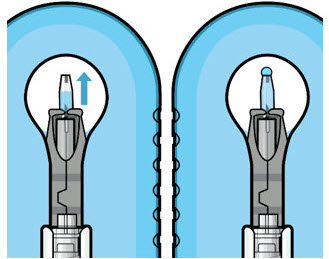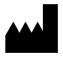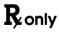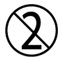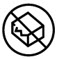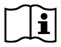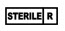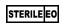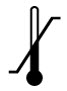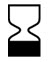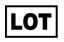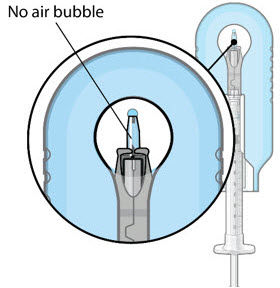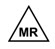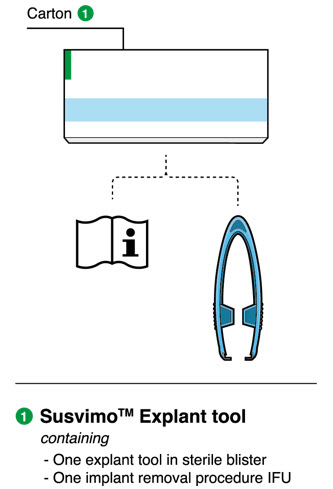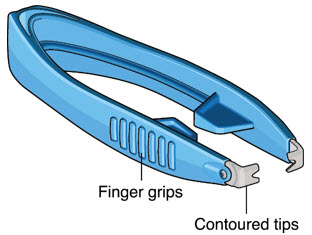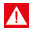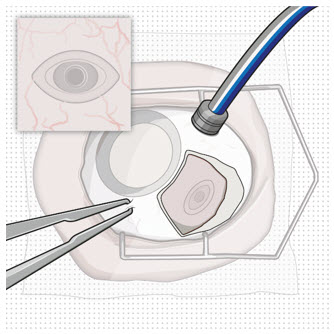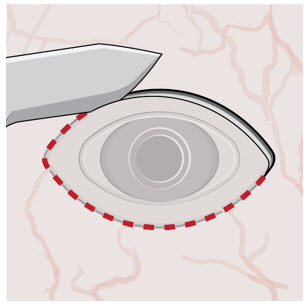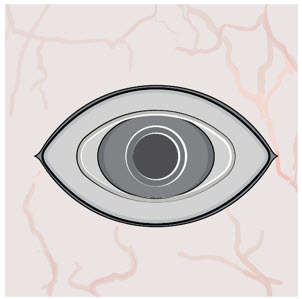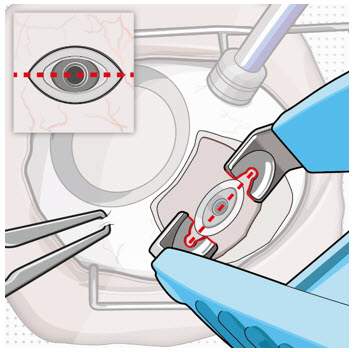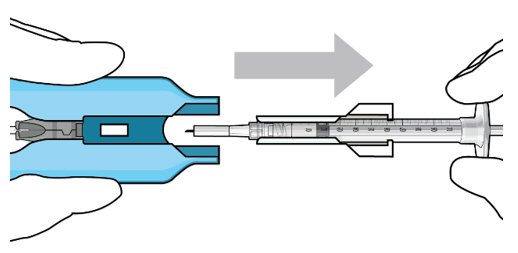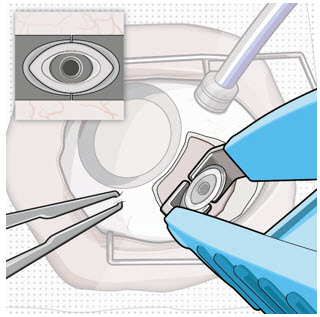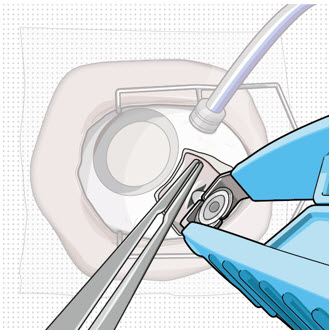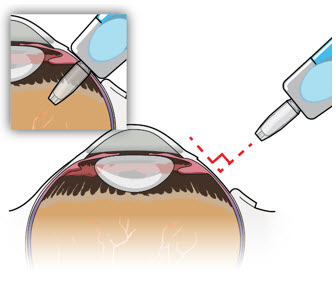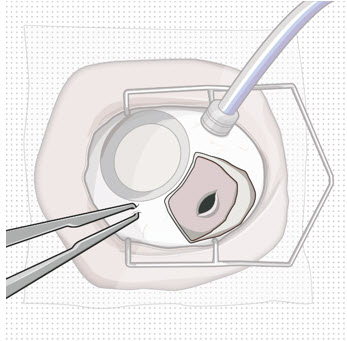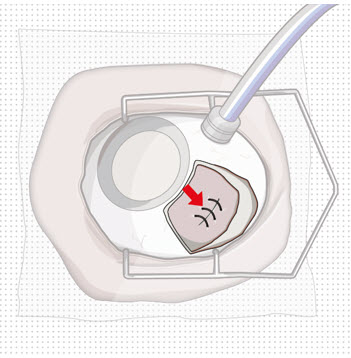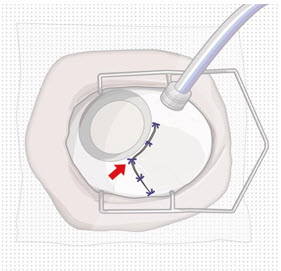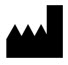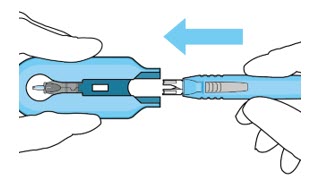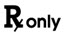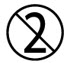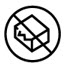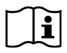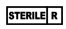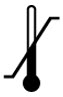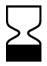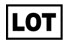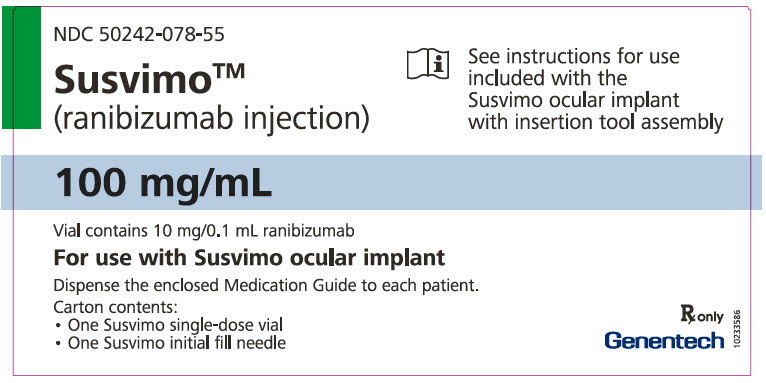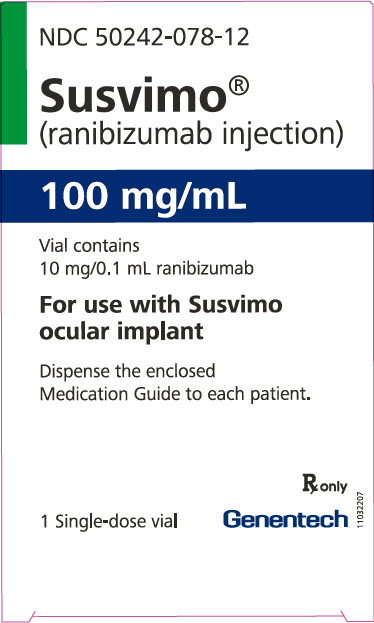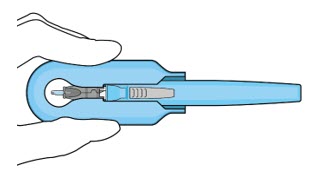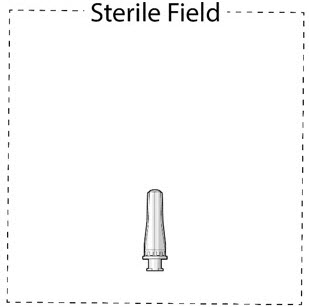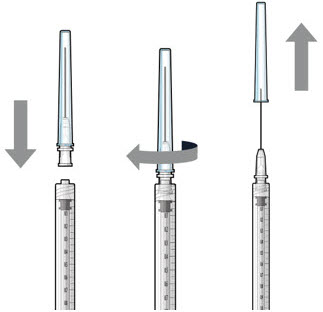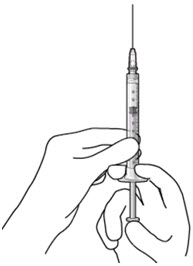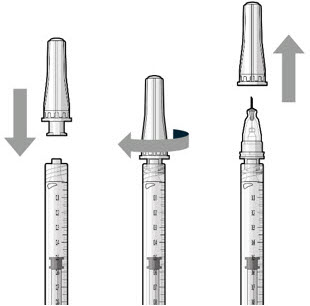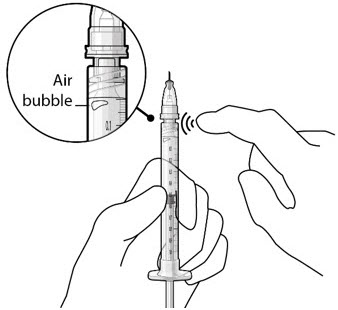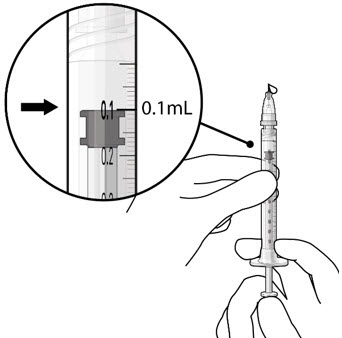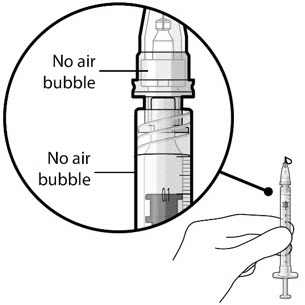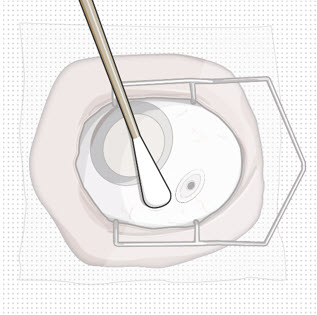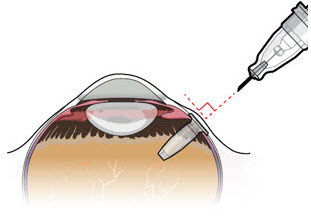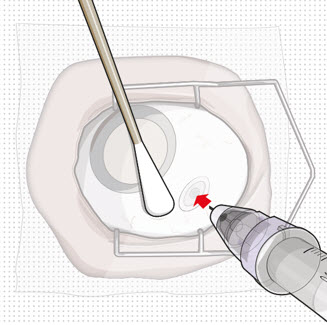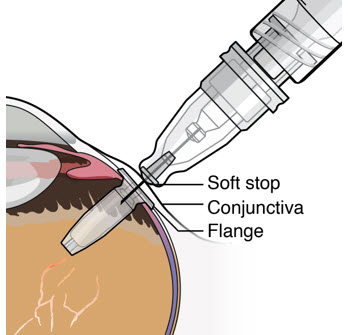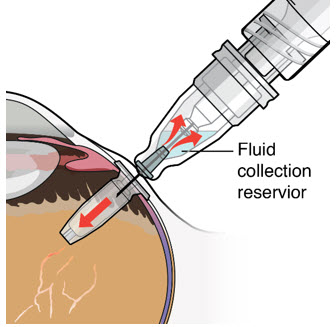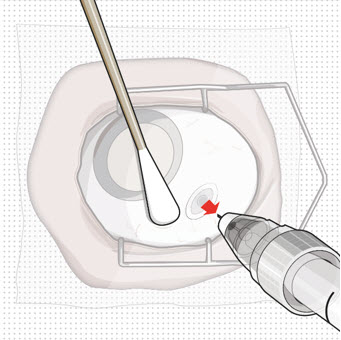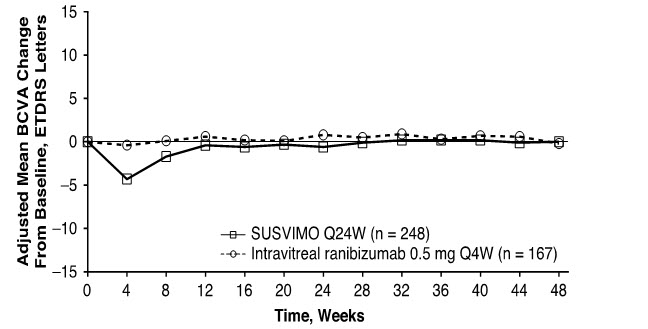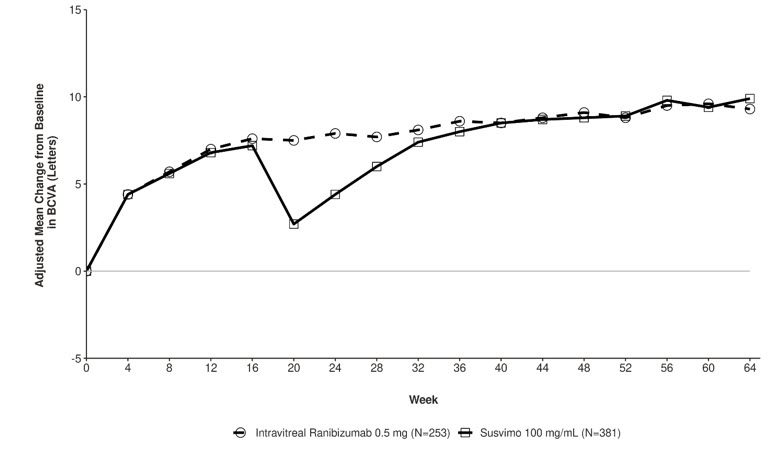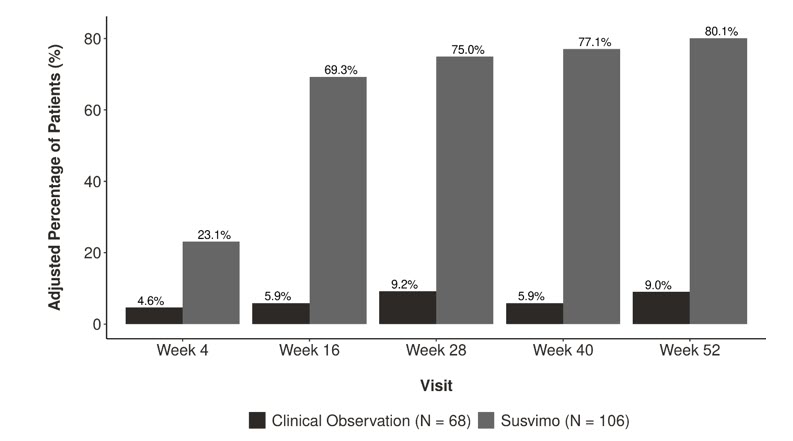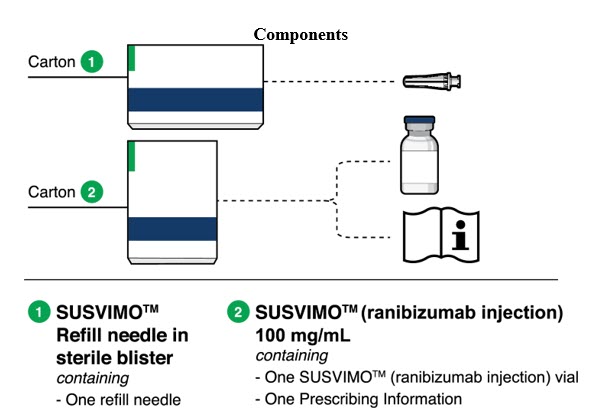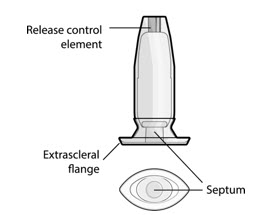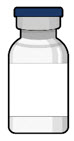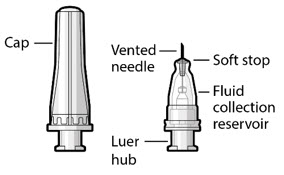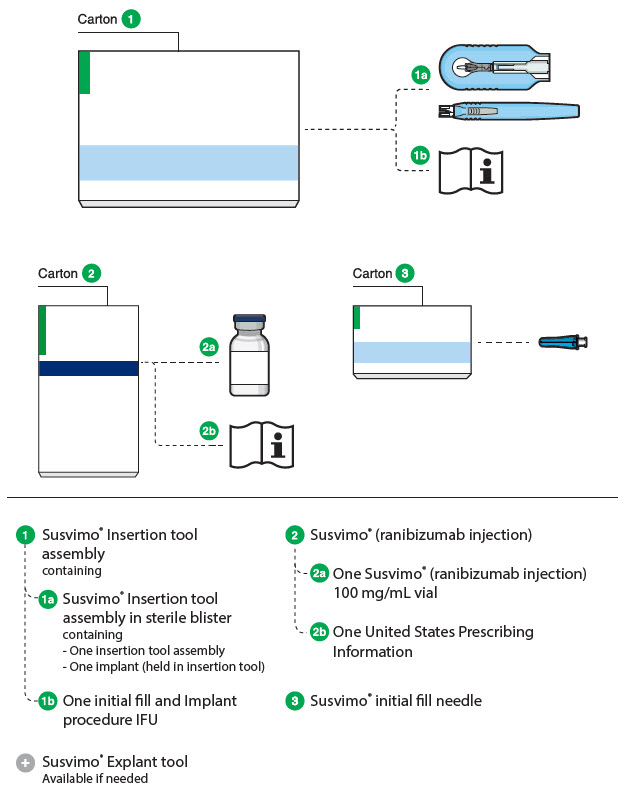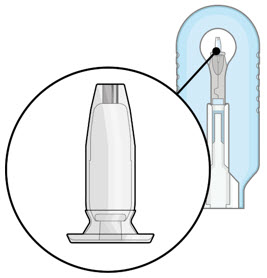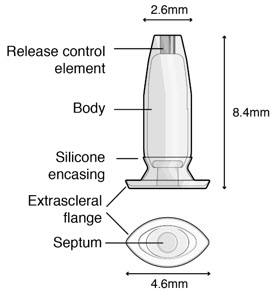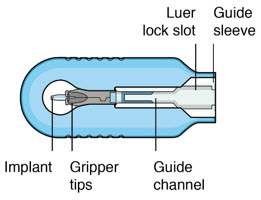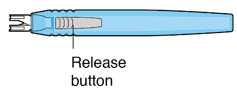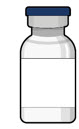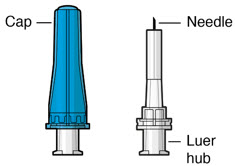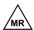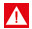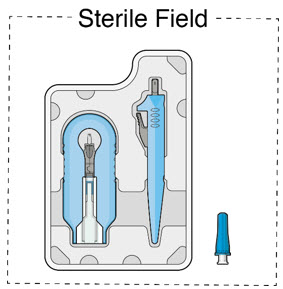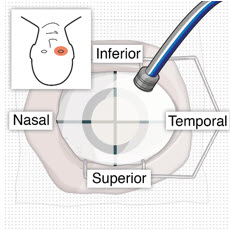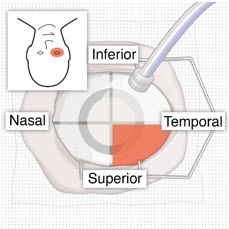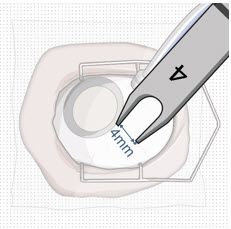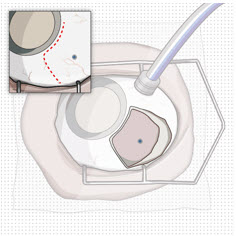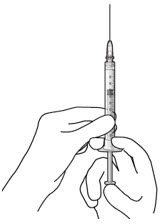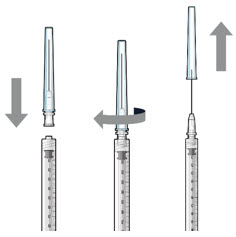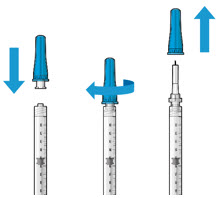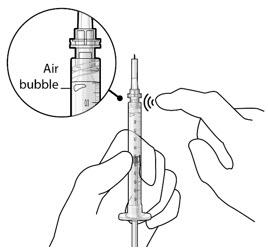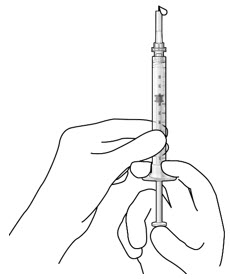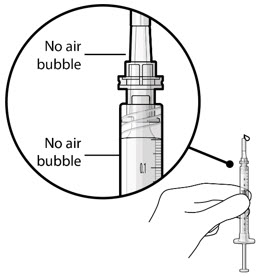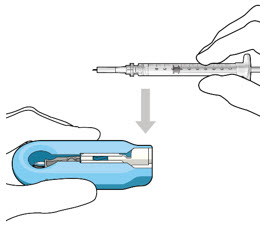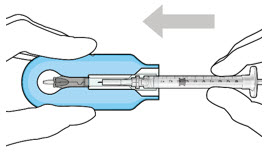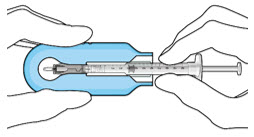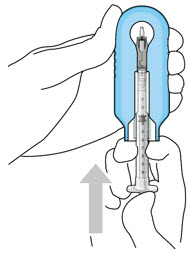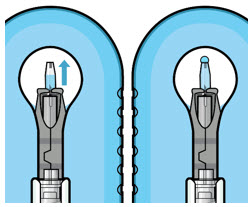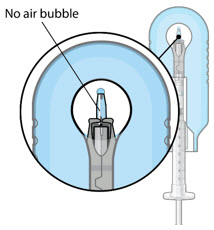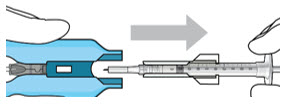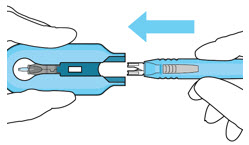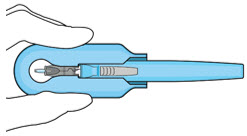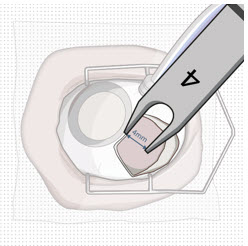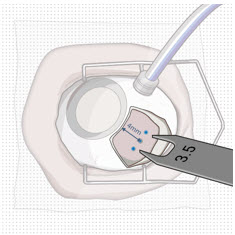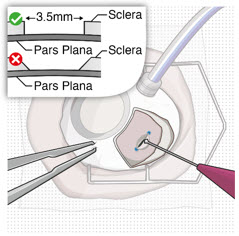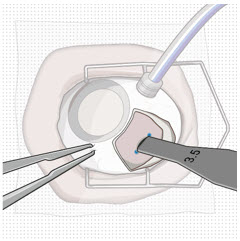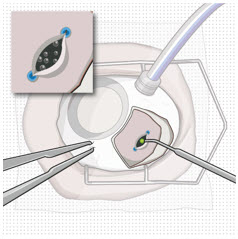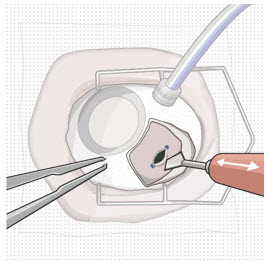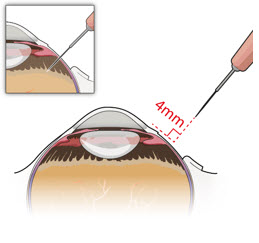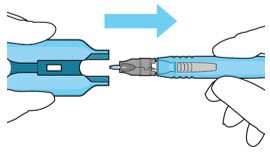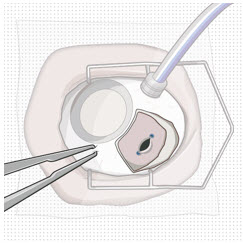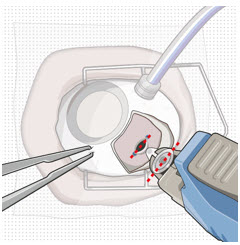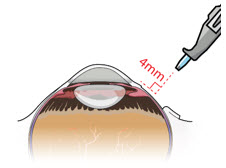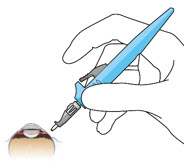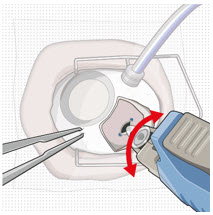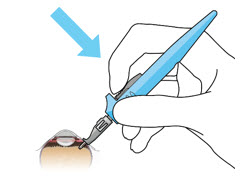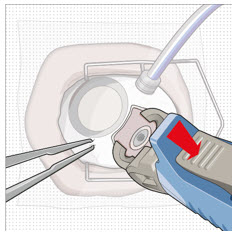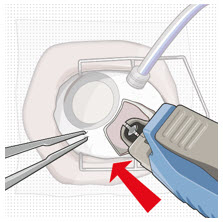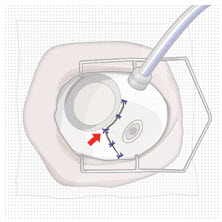 DRUG LABEL: Susvimo
NDC: 50242-078 | Form: INJECTION, SOLUTION
Manufacturer: Genentech, Inc.
Category: prescription | Type: HUMAN PRESCRIPTION DRUG LABEL
Date: 20251121

ACTIVE INGREDIENTS: RANIBIZUMAB 100 mg/1 mL
INACTIVE INGREDIENTS: HISTIDINE; SUCROSE; POLYSORBATE 20; WATER

HIGHLIGHTS OF PRESCRIBING INFORMATION

These highlights do not include all the information needed to use SUSVIMO safely and effectively. See full prescribing information for SUSVIMO.
SUSVIMO® (ranibizumab injection) for intravitreal use via SUSVIMO ocular implant
Initial U.S. Approval: 2006

WARNING: ENDOPHTHALMITIS

See full prescribing information for complete boxed warning.

The SUSVIMO implant has been associated with an up to 3-fold higher rate of endophthalmitis than monthly intravitreal injections of ranibizumab.

RECENT MAJOR CHANGES

Indications and Usage, Diabetic Macular Edema (DME) (1.2) | 2/2025
Indications and Usage, Diabetic Retinopathy (DR) (1.3) | 5/2025
Dosage and Administration (2.3, 2.9, 2.10) | 5/2025
Warnings and Precautions (5.1, 5.5, 5.6, 5.7, 5.8) | 5/2025
Warnings and Precautions (5.9) | 9/2025

1 INDICATIONS AND USAGE

SUSVIMO (ranibizumab injection) is a vascular endothelial growth factor (VEGF) inhibitor indicated for the treatment of patients with:

- Neovascular (wet) Age-related Macular Degeneration (AMD) who have previously responded to at least two intravitreal injections of a VEGF inhibitor (1.1).
- Diabetic Macular Edema (DME) who have previously responded to at least two intravitreal injections of a VEGF inhibitor (1.2).
- Diabetic Retinopathy (DR) who have previously responded to at least two intravitreal injections of a VEGF inhibitor (1.3).

2 DOSAGE AND ADMINISTRATION

- For intravitreal use via SUSVIMO ocular implant. (2.1)
- Neovascular (wet) Age-related Macular Degeneration (AMD) and Diabetic Macular Edema (DME)
  The recommended dose of SUSVIMO (ranibizumab injection) is 2 mg (0.02 mL of 100 mg/mL solution) continuously delivered via the SUSVIMO implant with refills every 24 weeks (approximately 6 months). (2.2)
- Diabetic Retinopathy (DR)
  The recommended dose of SUSVIMO (ranibizumab injection) is 2 mg (0.02 mL of 100 mg/mL solution) continuously delivered via the SUSVIMO implant with refills every 36 weeks (approximately 9 months). (2.3)
- Supplemental treatment with 0.5 mg intravitreal ranibizumab injection may be administered in the affected eye if clinically necessary. (2.4)
- Perform the initial implantation, refill-exchange, and implant removal (if necessary) procedures under strict aseptic conditions. (2.5, 2.6, 2.7, 2.8)

3 DOSAGE FORMS AND STRENGTHS

Injection: 100 mg/mL solution in a single-dose vial (3)

4 CONTRAINDICATIONS

- Ocular or periocular infections (4.1)
- Active intraocular inflammation (4.2)
- Hypersensitivity (4.3)

5 WARNINGS AND PRECAUTIONS

- The SUSVIMO implant and/or implant-related procedures have been associated with endophthalmitis, rhegmatogenous retinal detachment, implant dislocation, septum dislodgement, vitreous hemorrhage, conjunctival retraction, conjunctival erosion, and conjunctival bleb. Patients should be instructed to report signs or symptoms that could be associated with these events without delay. Additional surgical and/or medical management may be required. (5.1, 5.2, 5.3, 5.4, 5.5, 5.6, 5.7)
- Vitreous Hemorrhage: Temporarily discontinue antithrombotic medication prior to the implant insertion procedure to reduce the risk of vitreous hemorrhage. Vitrectomy may be needed. (5.5)
- Postoperative Decrease in Visual Acuity: A decrease in visual acuity usually occurs over the first two postoperative months. (5.8)

6 ADVERSE REACTIONS

The most common adverse reactions (≥ 10%) were conjunctival hemorrhage, conjunctival hyperemia, iritis, eye pain, conjunctival disorder, cataract and vitreous hemorrhage. (6.1)

To report SUSPECTED ADVERSE REACTIONS, contact Genentech at 1-888-835-2555 or FDA at 1-800-FDA-1088 or www.fda.gov/medwatch.

FULL PRESCRIBING INFORMATION

WARNING: ENDOPHTHALMITIS

The SUSVIMO implant has been associated with an up to 3-fold higher rate of endophthalmitis than monthly intravitreal injections of ranibizumab. Many of these events were associated with conjunctival retractions or erosions. Appropriate conjunctiva management and early detection with surgical repair of conjunctival retractions or erosions may reduce the risk of endophthalmitis. [see Contraindications (4.1), Warnings and Precautions (5.1)].

1 INDICATIONS AND USAGE

1.1 Neovascular (wet) Age-related Macular Degeneration (AMD)

SUSVIMO (ranibizumab injection) is indicated for the treatment of patients with Neovascular (wet) Age-related Macular Degeneration (AMD) who have previously responded to at least two intravitreal injections of a Vascular Endothelial Growth Factor (VEGF) inhibitor medication.

1.2 Diabetic Macular Edema (DME)

SUSVIMO (ranibizumab injection) is indicated for the treatment of patients with Diabetic Macular Edema (DME) who have previously responded to at least two intravitreal injections of a Vascular Endothelial Growth Factor (VEGF) inhibitor medication.

1.3 Diabetic Retinopathy (DR)

SUSVIMO (ranibizumab injection) is indicated for the treatment of patients with Diabetic Retinopathy (DR) who have previously responded to at least two intravitreal injections of a Vascular Endothelial Growth Factor (VEGF) inhibitor medication.

2 DOSAGE AND ADMINISTRATION

2.1 General Information

For Intravitreal Use via SUSVIMO ocular implant.

The SUSVIMO initial fill and ocular implant insertion and implant removal procedures must be performed under aseptic conditions by a physician experienced in vitreoretinal surgery. The SUSVIMO ocular implant must be surgically implanted in the eye or removed from the eye (if medically necessary) in an operating room using aseptic technique. See SUSVIMO Instructions for Use and the standardized steps to optimize surgical outcomes.

SUSVIMO refill-exchange procedures must be performed under aseptic conditions by a physician experienced in ophthalmic surgery [see Dosage and Administration (2.7)].

Do not administer SUSVIMO (ranibizumab injection) as a bolus intravitreal injection. Do not substitute SUSVIMO (ranibizumab injection) with other ranibizumab products.

Initial Fill: One SUSVIMO initial fill needle (34-gauge, with integrated 5 μm filter and blue cap) is included. A 5-micron sterile filter needle (19-gauge × 1½ inch), and a 1 mL Luer lock syringe are needed but not included.

Refill-Exchange: One SUSVIMO refill needle (34-gauge with integrated 5 μm filter and clear cap) is included. A 5-micron sterile filter needle (19-gauge × 1½ inch), and a 1 mL Luer lock syringe are needed but not included.

2.2 Neovascular (Wet) Age-Related Macular Degeneration (AMD) and Diabetic Macular Edema (DME)

The recommended dose of SUSVIMO (ranibizumab injection) is 2 mg (0.02 mL of 100 mg/mL solution) continuously delivered via the SUSVIMO ocular implant with refills administered every 24 weeks (approximately 6 months).

2.3 Diabetic Retinopathy (DR)

The recommended dose of SUSVIMO (ranibizumab injection) is 2 mg (0.02 mL of 100 mg/mL solution) continuously delivered via the SUSVIMO ocular implant with refills administered every 36 weeks (approximately 9 months).

2.4 Supplemental Treatment with Intravitreal Ranibizumab Injection

Supplemental treatment with 0.5 mg (0.05 mL of 10 mg/mL) intravitreal ranibizumab injection may be administered in the affected eye while the SUSVIMO implant is in place and if clinically necessary [see Clinical Studies (14)].

2.5 Ocular Implant Initial Fill

The implant initial fill procedure must be performed by a physician experienced in vitreoretinal surgery [see Dosage and Administration (2.1)]. The implant will be filled using aseptic technique with 0.02 mL of SUSVIMO (ranibizumab injection) prior to insertion of the implant into the patient's eye [see Dosage and Administration (2.6)].

Refer to the complete SUSVIMO Instructions for Use for the initial fill and implant procedure included in the insertion tool assembly carton for further details.

Use aseptic technique to carry out the following preparation steps prior to insertion of the ocular implant into the patient's eye:

Step 1: Gather the supplies needed.; - One SUSVIMO ocular implant with insertion tool assembly (included) - One SUSVIMO initial fill needle (34-gauge with integrated 5 μm filter) with blue cap (included) - One SUSVIMO (ranibizumab injection) 100 mg/mL vial (included) - One sterile 5-micron filter needle (19-gauge × 1½ inch) (not included) - One sterile 1 mL Luer Lock syringe (not included)
Step 2: Transfer Dose from Vial to Syringe
Note: | Use the filter needle (not included) to withdraw SUSVIMO (ranibizumab injection) from the vial. | Figure 1
Do not use the SUSVIMO initial fill needle for this step.; - Prepare SUSVIMO (ranibizumab injection) vial by removing the flip-off cap and disinfecting the rubber vial septum with alcohol. - Attach a filter needle to the syringe by screwing it tightly onto the Luer lock (see Figure 1). - Carefully remove the needle cap by pulling it straight off. - Using aseptic technique, withdraw all of the contents of the SUSVIMO (ranibizumab injection) vial through the filter needle into the syringe. |  | Figure 1
Step 3: Remove Air from Syringe; - With the filter needle attached, hold the syringe with the needle pointing up. - If there are any air bubbles, gently tap the syringe with your finger until the bubbles rise to the top (Figure 2). - Slowly push the plunger rod just until all air is expelled from the syringe and needle. - It is important to preserve as much drug as possible in order to completely fill the implant. - Remove and properly dispose of the filter needle after air is removed from syringe. |  | Figure2
Step 4: Attach SUSVIMO Initial Fill Needle Do not use the filter needle to fill the implant.; - Attach the SUSVIMO initial fill needle (included) firmly onto the syringe by screwing it tightly onto the Luer lock (see Figure 3). Ensure that the initial fill needle is attached to the syringe. - Carefully remove the needle cap by pulling straight off. - Do not wipe the needle at any time. |  | Figure 3
Step 5: Remove Any Remaining Air from Syringe; - With the initial fill needle attached, hold the syringe with the needle pointing up. If there are any air bubbles, gently tap the syringe with your finger until the bubbles rise to the top (see Figure 4). - Slowly push the plunger rod just until all air is expelled from the syringe and needle, and a drop of drug solution is seen at the needle tip (see Figure 5). |  | Figure 4 Figure 5
Note: | It is important to preserve as much drug as possible in order to completely fill the implant. | Figure 4 Figure 5
Step 6: Inspect the Syringe for Air Bubbles; - Inspect the syringe and the needle hub to ensure that no air bubbles are present (see Figure 6). - If air bubbles are present, continue to remove air from the syringe and reinspect. |  | Figure 6
Note: | Use the syringe within 15 minutes of removing all air to avoid ranibizumab drying in the needle and impeding fluid flow. Do not use the initial fill needle if the needle is clogged. | Figure 6
Step 7: Load Syringe into the Carrier Do not hold or push on the plunger rod of the syringe while inserting the needle into the implant septum.; - Retrieve insertion tool carrier with pre-positioned implant from the inner tray. - Align the syringe Luer lock above the Luer lock slot in the carrier to protect the needle from being damaged. - Lower the syringe into the carrier (see Figure 7). - Push the syringe forward until it stops, taking care to avoid touching the plunger rod (see Figure 8) - With the syringe loaded, (see Figure 9) the initial fill needle should now be penetrating the implant septum. |  | Figure 7: Align and lower the syringe into the carrier Figure 8: Push the syringe into the carrier Figure 9: Syringe with initial fill needle inserted through the implant septum
Step 8: Fill Ocular Implant with SUSVIMO (ranibizumab injection) Under Microscope; - Under the microscope, slowly administer SUSVIMO (ranibizumab injection) into the ocular implant by slightly tilting the carrier upwards (see Figure 10). - The ocular implant should be filled over approximately 5 to 10 seconds, to help avoid air entrapment in the implant reservoir. |  | Figure 10: Administer ranibizumab into the implant Figure 11: Dome of drug solution forms at tip of implant as viewed under magnification
Note: | When filling the ocular implant, drug solution should only exit the ocular implant from the release control element. If drug solution is leaking from the implant at a different location, such as the side of the implant, do not use the ocular implant. If fluid is leaking from the septum at the needle insertion site, the needle may not be fully penetrating the implant septum. Fully push the syringe forward before continuing to fill the ocular implant. | Figure 10: Administer ranibizumab into the implant Figure 11: Dome of drug solution forms at tip of implant as viewed under magnification
- Continue filling the ocular implant until the implant is completely full of drug solution and all air has been expelled as evidenced by a dome of drug solution formed at the tip of the implant on the release control element (see Figure 11). |  | Figure 10: Administer ranibizumab into the implant Figure 11: Dome of drug solution forms at tip of implant as viewed under magnification
Step 9: Inspect the Filled Ocular Implant Under the Microscope; - Inspect the ocular implant under the microscope to ensure that the ocular implant is completely full of drug solution (see Figure 12). |  | Figure 12: Proper appearance of implant after initial filling with ranibizumab
Note: | Minimize air bubbles within the implant reservoir as they may cause slower drug release. If an air bubble is present, it must be no larger than 1/3 of the widest diameter of the implant. If excess air is observed, do not use the ocular implant. | Figure 12: Proper appearance of implant after initial filling with ranibizumab
Note: | No more than 30 minutes should pass between the initial fill of the implant and the insertion into the patient's eye to ensure that the release control element remains saturated with SUSVIMO (ranibizumab injection). If SUSVIMO (ranibizumab injection) dries in the release control element, the implant may not release the drug properly into the vitreous after insertion. | Figure 12: Proper appearance of implant after initial filling with ranibizumab
Step 10: Remove the Syringe and Guide Sleeve from the Carrier; - Remove the syringe and guide sleeve from the carrier by pulling back on the syringe (see Figure 13). The syringe will be locked into the guide sleeve. - Properly dispose of the used syringe together with the needle and guide sleeve in a sharps disposal container or in accordance with local requirements. |  | Figure 13: Remove the syringe and guide sleeve from the insertion tool carrier
Step 11: Slide the Insertion Tool Handle into the Carrier; - Slide the insertion tool handle into the guide channel of the carrier, ensuring that both components are facing upwards (see Figure 14). - Push the handle forward as far as it will go into the gripper tips (see Figure 15). |  | Figure 14: Insert the handle into the insertion tool carrier Figure 15: Fully inserted handle
Note: | Do not withdraw the handle and implant until the eye is ready for insertion. Contact between the implant and any surface or object – even within the sterile field – may result in the introduction of a foreign body into the vitreous. | Figure 14: Insert the handle into the insertion tool carrier Figure 15: Fully inserted handle

2.6 Ocular Implant Insertion

SUSVIMO ocular implant insertion is a surgical procedure that is performed in an operating room. The procedure must be performed under aseptic conditions by a physician experienced in vitreoretinal surgery [see Dosage and Administration (2.1)].

The ocular implant is filled with SUSVIMO (ranibizumab injection) immediately prior to insertion. No more than 30 minutes should pass between the initial fill of the ocular implant and the insertion into the patient's eye.

After placing an infusion line in the eye, create at least a 6×6 mm peritomy of the conjunctiva and Tenon's capsule centered around the selected SUSVIMO implant location in the supero-temporal quadrant. Perform careful conjunctival incision, hemostasis of the underlying sclera, and generous undermining of Tenon's capsule. Using aseptic technique, fill the ocular implant [see Dosage and Administration (2.5)]. Using an MVR blade, create a full thickness dissection of the sclera 4 mm from the limbus until the pars plana is fully visible, with final target scleral incision length of 3.5 mm. Using a 532 nm laser endoprobe, apply contiguous, overlapping laser spots starting at 300 mW 1000 ms along the full length of the exposed pars plana and repeat until complete ablation is achieved. Pass a 3.2 mm slit knife perpendicularly through the center of the scleral dissection to open the underlying pars plana. Use the insertion tool to slowly insert the SUSVIMO implant into the sclero-pars plana incision perpendicular to the globe, ensuring that the long axis of the implant flange is properly aligned with the sclero-pars plana incision. Using the closed gripper tips of the insertion tool, seat the implant flush against the sclera. Clean any residual vitreous around the implant flange using a vitrector. Suture both Tenon's capsule and conjunctiva, using scleral anchoring at the apex of the peritomy, ensuring complete coverage of the implant flange. Refer to the complete SUSVIMO Instructions for Use for the initial fill and implant procedure included in the insertion tool assembly carton for further details.

2.7 Ocular Implant Removal

Removal of the SUSVIMO ocular implant is a surgical procedure that is performed in an operating room. The procedure must be performed under aseptic conditions by a physician experienced in vitreoretinal surgery [see Dosage and Administration (2.1)].

After placing an infusion line in the eye, create at least a 6×6 mm peritomy of the conjunctiva and Tenon's capsule around the SUSVIMO ocular implant flange. Remove any fibrous capsule or scar tissue that may have formed over the implant flange and septum using scalpel and forceps. With the explant tool oriented perpendicular to the globe, align the contoured tips with the long axis of the implant flange and grasp underneath the implant flange. Once the implant is secured in the explant tool, pull the implant from the eye in a perpendicular motion. Clear any vitreous prolapse present within or around the scleral wound using a vitrector. Completely close the scleral incision with multiple non-absorbable sutures. Close the Tenon's capsule and conjunctiva to completely cover the scleral incision. Refer to the complete Instructions for Use for the implant removal procedure included in the explant tool carton for further details.

2.8 Ocular Implant Refill-Exchange Procedure

The SUSVIMO ocular implant refill-exchange procedure must be performed under strict aseptic conditions by a physician experienced in ophthalmic surgery [see Dosage and Administration (2.1)]. This includes the use of a surgical mask, sterile gloves, and a lid speculum.

Prior to and after the refill-exchange procedure, perform a dilated slit lamp exam and/or dilated indirect ophthalmoscopy to inspect the implant in the vitreous cavity through the pupil to identify if dislodgement of the implant septum has occurred [see Figure 33 and Warnings and Precautions (5.4)]. If the septum has dislodged, any further refill-exchange procedures should not be performed because normal device functioning cannot be assured. Discontinue treatment with SUSVIMO (ranibizumab injection) following septum dislodgement and consider implant removal should the benefit of the removal procedure outweigh the risk.

Step 1: Gather the supplies needed.

- One SUSVIMO Refill Needle (34-gauge with a 5 µm integrated filter) with clear cap (included)
- One SUSVIMO (ranibizumab injection) 100 mg/mL vial (included)
- One sterile 1 mL Luer Lock syringe (not included)
- One sterile 5-micron filter needle (19-gauge × 1½ inch) (not included)

Additional materials required to perform the procedure but are not provided are:

- Anesthetic ophthalmic solutions
- Ophthalmic broad-spectrum microbicide solution
- Cotton tips and gauze
- Sterile powder free gloves
- Face masks
- Lid speculum
- Magnification such as visor or loupes
- Task lighting
- Indirect ophthalmoscope and lens
- Sterile drape (optional for refill-exchange procedure)

Step 2: Inspect Packaging and Components

- Prior to use in the clinic, inspect the packaging of the components for damage. Do not use if the sterility has been compromised or the contents have been dropped, damaged, or tampered with.
- Check the expiration date printed on the label.
- Remove the vial from the carton. Note: the outside of the vial is not sterile.
- Use aseptic technique to open packaging and remove the sterile refill needle from the tray.
- Inspect components and place onto sterile field (see Figure 16).

Figure 16

Step 3: Inspect SUSVIMO (ranibizumab injection)

- Visually inspect the contents of the SUSVIMO (ranibizumab injection) vial for particulate matter and discoloration.
- SUSVIMO should be colorless to slightly brownish

Do not use if particulate, cloudiness, or discoloration are visible.

Step 4: Patient Preparation

- Dilate the pupil of the eye.
- Perform slit lamp examination and/or indirect ophthalmoscopy to inspect the implant and its components in the vitreous cavity through the dilated pupil.
- Position the patient on exam chair in the supine position at approximately 20° to 30° angle for optimal visualization of the implant.
- Apply a broad-spectrum microbicide to the periocular skin, eyelid, and ocular surface prior to the refill-exchange procedure. The use of a sterile drape is up to the physician's discretion.
- Perform the procedure under topical anesthesia.
- If needed, subconjunctival anesthesia may be administered in the nasal quadrant, away from the implant.

Step 5: Transfer Dose from Vial to Syringe

Figure 17

Note:

Use the filter needle to withdraw SUSVIMO (ranibizumab injection) from the vial.

Do not use the SUSVIMO refill needle for this step.

- Prepare ranibizumab vial by removing the flip-off cap and disinfecting the rubber vial septum with alcohol.
- Attach a filter needle to the syringe by screwing it tightly onto the Luer lock (see Figure 17).
- Carefully remove the needle cap by pulling it straight off.
- Using aseptic technique, withdraw all of the contents of the SUSVIMO (ranibizumab injection) vial through the filter needle into the syringe.

Step 6: Remove Air from Syringe

- With the filter needle attached, hold the syringe with the needle pointing up.
- If there are any air bubbles, gently tap the syringe with your finger until the bubbles rise to the top (Figure 18).
- Slowly push the plunger rod just until the air is expelled from the syringe and needle.
  - It is important to preserve as much drug as possible in order to completely refill the implant
- Remove and properly dispose of the filter needle after air is removed from the syringe.

Figure 18

Step 7: Attach SUSVIMO Refill Needle
Do not use the filter needle to fill the implant.

- Attach the SUSVIMO refill needle firmly onto the syringe by screwing it tightly onto the Luer lock (see Figure 19). Ensure that the refill needle is attached to the syringe.
- Carefully remove the needle cap, pulling straight off to avoid damage to the needle cannula.
- Do not wipe the needle at any time.

Figure 19

Step 8: Remove Any Remaining Air from Syringe and Adjust Drug Dose

- With the refill needle attached, hold the syringe with the needle pointing up.
- If there are any air bubbles, gently tap the syringe with your finger until the bubbles rise to the top (see Figure 20).
- Slowly push the plunger rod until all air is expelled from the syringe and needle and the uppermost edge of the black plunger tip is aligned with the 0.1 mL dose mark (see Figure 21).

Figure 20
Figure 21

Step 9: Inspect the Syringe for Air Bubbles

Figure 22

Note:

Ensure no air bubbles are present in the syringe and needle hub. Air injected into the implant could result in slower drug release.

- Inspect the syringe and the needle hub using magnification to ensure that no air bubbles are present (see Figure 22).

Note:

Use the syringe within 15 minutes of removing all air and adjusting the drug dose to avoid drug solution drying in the needle and impeding fluid flow.
Do not use the refill needle or syringe if the needle is clogged.

Step 10: Stabilize the globe and orient the refill needle

Figure 23 Figure 24

Note:

Perform the refill-exchange procedure using magnification (e.g., loupes, reading glasses, magnifiers) for visual assistance.

- After placing the lid speculum in the eye, stabilize the globe with a cotton-tipped applicator to minimize eye movement (see Figure 23).
  - Recommend standing on the contralateral side of the implanted eye, with the patient looking down and toward their nose to optimally expose the implant.
- Orient the refill needle perpendicular to the globe (see Figure 24).

Step 11: Insert the Refill Needle

Figure 25
Figure 26

Note:

Insert needle at the very center of the implant septum and perpendicular to the implant to ensure the needle inserts fully. Do not maneuver if there is resistance as it will bend the needle.

Do not use a bent refill needle; replace if bent or if damage is suspected.

- Targeting the center of the implant septum, insert the refill needle perpendicularly through the conjunctiva and into the implant septum (see Figure 25).
  - If excessive resistance, withdraw the refill needle. Orient and insert again.
  - Do not twist when encountering conjunctiva and Tenon's capsule to gain access to the septum, as damage to the overlying tissue and to the septum of the device may result.
- Continue inserting the needle until the soft stop of the refill needle makes physical contact with the conjunctiva (see Figure 26) to provide a tactile cue that optimal contact has been made.

Step 12: Refill the SUSVIMO Implant

- Refill the implant slowly, by delivering the entire contents of the syringe into the implant, over approximately 5 to 10 seconds, to avoid pressure build-up in the implant reservoir. The soft stop of the refill needle must remain in contact with the conjunctiva throughout the procedure.
- As ranibizumab is administered into the implant, existing solution from the implant should immediately begin to fill the refill needle fluid collection chamber (see Figure 27).
- If fluid is not observed collecting in the refill needle fluid collection reservoir, stop injecting and ensure the refill needle is inserted into the center of the implant septum at a perpendicular angle and the soft stop is in contact with the conjunctiva.
- Administer all of the syringe contents in order to achieve the target replacement ranibizumab concentration in the implant reservoir.

Figure 27

Step 13: Withdraw the Syringe

- Withdraw the syringe perpendicular to the globe to avoid damaging the septum (see Figure 28).
- A cotton-tipped applicator may be used to provide counter traction to the conjunctiva during needle withdrawal.

Figure 28

Step 14: Dispose of the Used Components

- Do not recap the needle or detach it from the syringe. Dispose of the used syringe together with the refill needle in a sharps disposal container or in accordance with local requirements.

Step 15: Perform Indirect Ophthalmoscopy

- Perform dilated indirect ophthalmoscopy (and slit lamp exam as needed) to ensure continued proper position of the implant and its components (e.g., septum) in the vitreous cavity and to examine for complications.

2.9 Delayed or Missed Doses

For patients with AMD or DME, if a planned dose (refill-exchange) of SUSVIMO (ranibizumab injection) is missed, it should be administered as soon as possible and the subsequent refill-exchange procedures should be performed 24 weeks (approximately 6 months) thereafter.

For patients with DR, if a planned dose (refill-exchange) of SUSVIMO (ranibizumab injection) is missed, it should be administered as soon as possible and the subsequent refill-exchange procedures should be performed 36 weeks (approximately 9 months) thereafter.

2.10 Dosage (Refill-Exchange) Modifications for Adverse Reactions

Table 1 describes dosage modifications for specific adverse Reactions [see Warnings and Precautions (5)]. No dosage reductions for SUSVIMO are recommended.

Table 1: Dosage (Refill-Exchange) Modifications for Adverse Reactions
Adverse Reactions | Dosage Modification
Intraocular inflammation ≥ 1 + cells or flare | Withhold dose (refill-exchange)
Sight threatening events (e.g., rhegmatogenous retinal detachment, vitreous hemorrhage, unexplained vision loss, etc.) | Withhold dose (refill-exchange)
Local infections of either eye | Withhold dose (refill-exchange)
Infectious endophthalmitis | Withhold dose (refill-exchange)
Severe systemic infection | Withhold dose (refill-exchange)
Observed damage to the implant | Withhold dose (refill-exchange) and consider SUSVIMO implant removal [see Dosage and Administration (2.8, 2.9)].

3 DOSAGE FORMS AND STRENGTHS

Injection: 100 mg/mL, clear to slightly opalescent, colorless to slightly brownish solution in a single-dose vial

4 CONTRAINDICATIONS

4.1 Ocular or Periocular Infections

SUSVIMO (ranibizumab injection) is contraindicated in patients with ocular or periocular infections.

4.2 Active Intraocular Inflammation

SUSVIMO (ranibizumab injection) is contraindicated in patients with active intraocular inflammation.

4.3 Hypersensitivity

SUSVIMO (ranibizumab injection) is contraindicated in patients with known hypersensitivity to ranibizumab products or any of the excipients in SUSVIMO (ranibizumab injection).

5 WARNINGS AND PRECAUTIONS

The SUSVIMO implant and/or implant-related procedures have been associated with endophthalmitis, rhegmatogenous retinal detachment, implant dislocation, septum dislodgement, vitreous hemorrhage, conjunctival erosion, conjunctival retraction, and conjunctival blebs. Patients should be instructed to report any signs or symptoms that could be associated with these events without delay. In some cases, these events can present asymptomatically. The implant and the tissue overlying the implant flange should be monitored routinely following the implant insertion, and refill-exchange procedures to permit early medical or surgical intervention as necessary. Special precautions need to be taken when handling SUSVIMO components [see How Supplied/Storage and Handling (16.3)].

5.1 Endophthalmitis

In the active comparator period of controlled clinical trials in AMD, the ranibizumab implant has been associated with a 3-fold higher rate of endophthalmitis than monthly intravitreal injections of ranibizumab (1.7% in the SUSVIMO arm vs 0.5% in the intravitreal arm). When including extension phases of clinical trials, 2% (11/555) of patients receiving the ranibizumab implant experienced an episode of endophthalmitis. Reports occurred between days 5 and 853, with a median of 173 days. Many, but not all, of the cases of endophthalmitis reported a preceding or concurrent conjunctival retraction or erosion event.

In the active comparator period of the controlled clinical trial in DME, 0% of patients in the SUSVIMO arm compared to 0.3% in the intravitreal arm experienced an episode of endophthalmitis. When including the extension phase of the clinical trial, 0.7% (4/556) of patients receiving the ranibizumab implant experienced an episode of endophthalmitis. Reports occurred between days 625 and 1016, with a median of 824 days.

In the period with an observational comparator arm of the clinical trial in DR, there were no patients (0/105) in the SUSVIMO arm who experienced an episode of endophthalmitis [see Clinical Studies (14.3)]. When including the extension phase of the clinical trial 0.8% (1/128) patients receiving the ranibizumab implant experienced an episode of endophthalmitis, with the event reported on day 695.

Endophthalmitis should be treated promptly in an effort to reduce the risk of vision loss and maximize recovery. The SUSVIMO (ranibizumab injection) dose (refill-exchange) should be delayed until resolution of endophthalmitis [see Dosage and Administration (2.10) and Adverse Reactions (6.1)].

Patients should not have an active or suspected ocular or periocular infection or severe systemic infection at the time of any SUSVIMO implant or refill procedure. Appropriate intraoperative handling followed by secure closure of the conjunctiva and Tenon's capsule, and early detection and surgical repair of conjunctival erosions or retractions and strict/controlled aseptic technique conditions throughout refill-exchange procedures may reduce the risk of endophthalmitis [see Dosage and Administration (2.1) and Warnings and Precautions (5.5)].

5.2 Rhegmatogenous Retinal Detachment

Rhegmatogenous retinal detachments have occurred in clinical trials of SUSVIMO and may result in vision loss. Rhegmatogenous retinal detachments should be promptly treated with an intervention (e.g., pneumatic retinopexy, vitrectomy, or laser photocoagulation). SUSVIMO (ranibizumab injection) dose (refill-exchange) should be delayed in the presence of a retinal detachment or retinal break [see Dosage and Administration (2.10)].

Careful evaluation of the retinal periphery is recommended to be performed, and any suspected areas of abnormal vitreo-retinal adhesion or retinal breaks should be treated before inserting the implant in the eye.

5.3 Implant Dislocation

In clinical trials, the device has dislocated/subluxated into the vitreous cavity or has extended outside the vitreous cavity into or beyond the subconjunctival space. Device dislocation requires urgent surgical intervention. Strict adherence to the scleral incision length and appropriate targeting of the pars plana during laser ablation may reduce the risk of implant dislocation.

5.4 Septum Dislodgement

In clinical trials, a type of implant damage where the septum has dislodged into the implant body has been reported. Perform a dilated slit lamp exam and/or dilated indirect ophthalmoscopy to inspect the implant in the vitreous cavity through the pupil prior to and after the refill-exchange procedure to identify if septum dislodgement has occurred. Discontinue treatment with SUSVIMO (ranibizumab injection) following septum dislodgement and consider implant removal should the benefit of the removal procedure outweigh the risk [see Dosage and Administration (2.9)]. The benefits and risks of retaining, removing, or removing and replacing an implant with a dislodged septum are not well characterized.

Appropriate handling and insertion of the refill needle into the septum (avoid twisting and/or rotation) is required to minimize the risk of septum dislodgement [see Dosage and Administration (2.8)].

5.5 Vitreous Hemorrhage

Vitreous hemorrhages may result in temporary vision loss. Vitrectomy may be needed in the case of a non-clearing vitreous hemorrhage [see Dosage and Administration (2.10)].

In clinical trials of SUSVIMO including the extension phases in patients with AMD, vitreous hemorrhages were reported in 5.2% (23/443) of patients receiving SUSVIMO.

In the clinical trial of SUSVIMO including the extension phases in patients with DME, vitreous hemorrhages were reported in 10.1% (56/556) of patients receiving SUSVIMO.

In the clinical trial of SUSVIMO including the extension phase in patients with DR, vitreous hemorrhages were reported in 9.4% (12/128) of patients receiving SUSVIMO.

The majority of these hemorrhages occurred within the first post-operative month following surgical implantation and the majority of vitreous hemorrhages resolved spontaneously.

Patients on antithrombotic medication (e.g., oral anticoagulants, aspirin, nonsteroidal anti-inflammatory drugs) may be at increased risk of vitreous hemorrhage. Antithrombotic medications are recommended to be temporarily interrupted prior to the implant insertion procedure. The SUSVIMO (ranibizumab injection) dose (refill-exchange) should be delayed in the event of sight-threatening vitreous hemorrhage.

The use of pars plana laser ablation and scleral cauterization should be performed to reduce the risk of vitreous hemorrhage.

5.6 Conjunctival Erosion or Retraction

A conjunctival erosion is a full thickness degradation or breakdown of the conjunctiva in the area of the implant flange. A conjunctival retraction is a recession or opening of the limbal and/or radial peritomy. Conjunctival erosions or retractions have been associated with an increased risk of endophthalmitis, especially if the implant becomes exposed. Surgical intervention (e.g., conjunctival/Tenon's capsule repair) is recommended to be performed in case of conjunctival erosion or retraction with or without exposure of the implant flange.

In clinical trials of SUSVIMO including the extension phases in patients with AMD, 3.6% (16/443) of patients receiving SUSVIMO reported conjunctival erosion and 1.6% (7/443) of patients receiving SUSVIMO reported conjunctival retraction in the study eye.

In the clinical trial of SUSVIMO including the extension phases of patients with DME, 2.2% (12/556) of patients receiving SUSVIMO reported conjunctival erosion and 1.3% (7/556) of patients receiving SUSVIMO reported conjunctival retraction in the study eye.

In the clinical trial of SUSVIMO including the extension phase in patients with DR, 2.3% (3/128) of patients receiving SUSVIMO reported conjunctival erosion and 1.6% (2/128) of patients receiving SUSVIMO reported conjunctival retraction in the study eye.

Appropriate intraoperative handling of conjunctiva and Tenon's capsule to preserve tissue integrity and secure closure of peritomy while ensuring placement of sutures away from implant edge may reduce the risk of conjunctival erosion or retraction. The implant and the tissue overlying the implant flange should be monitored routinely following the implant insertion.

5.7 Conjunctival Bleb

A conjunctival bleb is an encapsulated elevation of the conjunctiva above the implant flange, which may be secondary to subconjunctival thickening or fluid. Conjunctival blebs may require surgical management to avoid further complications, especially if the implant septum is no longer identifiable due to the conjunctival bleb.

In clinical trials of SUSVIMO including the extension phases in patients with AMD, 5.9% (26/443) of patients receiving SUSVIMO reported conjunctival bleb/conjunctival filtering bleb leak in the study eye.

In the clinical trial of SUSVIMO including the extension phases in patients with DME, 9% (50/556) of patients receiving SUSVIMO reported conjunctival bleb/conjunctival filtering bleb leak in the study eye.

In the clinical trial of SUSVIMO including the extension phase in patients with DR, 3.9% (5/128) of patients receiving SUSVIMO reported conjunctival bleb/conjunctival filtering bleb leak in the study eye.

Strict adherence to the scleral incision length, appropriate intraoperative handling of conjunctiva and Tenon's capsule to preserve tissue integrity and secure closure of peritomy, and proper seating of the refill needle during refill-exchange procedures may reduce the risk of conjunctival bleb.

5.8 Postoperative Decrease in Visual Acuity

Visual acuity was decreased by 4 letters on average in the first postoperative month and 2 letters on average in the second postoperative month following initial implantation of SUSVIMO in patients with AMD [see Clinical Studies (14.1)].

Visual acuity was decreased by 7 letters on average in the first postoperative month and 3 to 4 letters on average in the second postoperative month following initial implantation of SUSVIMO in patients with DME and DR [see Clinical Studies (14.2 and 14.3)].

5.9 Postoperative Intraocular Inflammation

Postoperative intraocular inflammation has occurred following SUSVIMO implantation. The majority of cases occurred during the first week following implantation and resolved within the first month.

5.10 Air Bubbles Causing Improper Filling of the Implant

Minimize air bubbles within the implant reservoir as they may cause slower drug release. During the initial fill procedure, if an air bubble is present, it must be no larger than 1/3 of the widest diameter of the implant. If excess air is observed after initial fill, do not use the implant. During the refill-exchange procedure, if excess air is present in the syringe and needle do not use the syringe and needle. If excess air bubbles are observed after the refill-exchange procedure, consider repeating the refill-exchange procedure.

5.11 Deflection or Movement of the Implant

Use caution when performing ophthalmic procedures (e.g., B-scan ophthalmic ultrasound, scleral depression, or gonioscopy) that may cause deflection or movement of the implant and subsequent injury.

6 ADVERSE REACTIONS

The following adverse reactions are discussed in greater detail in other sections of the label:

- Endophthalmitis [see Warnings and Precautions (5.1)]
- Rhegmatogenous Retinal Detachment [see Warnings and Precautions (5.2)]
- Implant Dislocation [see Warnings and Precautions (5.3)]
- Septum Dislodgement [see Warnings and Precautions (5.4)]
- Vitreous Hemorrhage [see Warnings and Precautions (5.5)]
- Conjunctival Erosion or Retraction [see Warnings and Precautions (5.6)]
- Conjunctival Bleb [see Warnings and Precautions (5.7)]
- Postoperative Decrease in Visual Acuity [see Warnings and Precautions (5.8)]

6.1 Clinical Trials Experience

Because clinical trials are conducted under widely varying conditions, adverse reaction rates observed in one clinical trial of a drug cannot be directly compared with rates in the clinical trials of the same or another drug and may not reflect the rates observed in practice.

The data below (Table 2) reflect exposure of 248 patients with AMD in the Archway study through Week 40, 320 patients with DME in the Pagoda study up to Week 64, and 105 patients with DR in the Pavillion study through Week 52 following the SUSVIMO initial fill and implant insertion, refill, and implant removal (if necessary) procedures.

In clinical trials of SUSVIMO in AMD patients, the most common (≥ 10%) adverse reactions up to Week 40 were conjunctival hemorrhage (72%), conjunctival hyperemia (26%), iritis (23%), and eye pain (10%). Septum dislodgement was reported in 0.4% of the AMD patient population.

In clinical trials of SUSVIMO in DME patients, patient population the most common (≥ 10%) adverse reactions up to Week 64 were conjunctival hemorrhage (62%), conjunctival hyperemia (15%), iritis (14%), eye pain (13%), cataract (11%), conjunctival disorder (10%) and vitreous hemorrhage (10%).

In clinical trials of SUSVIMO in DR patients, the most common (≥ 10%) adverse reactions up to Week 52 were conjunctival hemorrhage (73%), conjunctival disorder (14%), iritis (12%) and conjunctival hyperemia (11%).

Table 2 Adverse Reactions occurring in ≥ 4% of patients in the SUSVIMO arm
Adverse Reactions | AMD Week 40 |  | DME Week 64 |  | DR Week 52
Adverse Reactions | SUSVIMO n = 248 | Intravitreal ranibizumab n = 167 | SUSVIMO n = 320 | Intravitreal ranibizumab 0.5 mg n = 314 | SUSVIMO n = 105
Conjunctival hemorrhage | 72% | 6% | 62% | 18% | 73%
Conjunctival hyperemia | 26% | 2% | 15% | 0 | 11%
Iritis [Iritis includes: iritis, anterior chamber flare, anterior chamber inflammation, and anterior chamber cell.] | 23% | 0.6% | 14% | 2% | 12%
Eye pain | 10% | 5% | 13% | 6% | 9%
Conjunctival disorder [Conjunctival disorder includes: conjunctival adhesion, conjunctival disorder, conjunctival edema, conjunctival erosion, conjunctival retraction, and subconjunctival fibrosis.] | 9% | 0 | 10% | 0.3% | 14%
Vitreous floaters | 9% | 2% | 4% | 5% | 2%
Conjunctival bleb/ filtering bleb leak [Conjunctival bleb/filtering bleb leak includes: conjunctival bleb, conjunctival filtering bleb leak, conjunctival cyst, subconjunctival cyst, and implant site cyst.] | 8% | 0 | 8% | 0 | 2%
Foreign body sensation in eyes | 7% | 1% | 3% | 2% | 9%
Headache [Headache includes: headache and procedural headache.] | 6% | 2% | 6% | 4% | 9%
Hypotony of eye | 6% | 0 | 3% | 0 | 0
Vitreous detachment | 6% | 5% | 8% | 5% | 9%
Vitreous hemorrhage | 5% | 2% | 10% | 2% | 6%
Cataract [Cataract includes: cataract, cortical cataract, nuclear cataract, and subcapsular cataract.] | 4% | 4% | 11% | 7% | 7%
Corneal disorder | 4% | 0 | 1% | 0 | 1%
Corneal abrasion [Corneal abrasion includes: corneal abrasion and vital dye staining cornea present.] | 4% | 0.6% | 4% | 1% | 4%
Corneal edema | 4% | 0 | 4% | 0.3% | 4%

In clinical trials of SUSVIMO, hyphema was reported in 0.4% of AMD patients, 1.9% of DME patients, and 1.9% of DR patients.

8 USE IN SPECIFIC POPULATIONS

8.1 Pregnancy

Risk Summary

There are no adequate and well-controlled studies of SUSVIMO (ranibizumab injection) administration in pregnant women. Administration of ranibizumab to pregnant monkeys throughout the period of organogenesis resulted in a low incidence of skeletal abnormalities at intravitreal doses up to 41 times the human exposure (based on serum levels following the recommended clinical dose). No skeletal abnormalities were observed at serum trough levels similar to the human exposure after a single eye treatment at the recommended clinical dose (see Data).

Animal reproduction studies are not always predictive of human response, and it is not known whether ranibizumab can cause fetal harm when administered to a pregnant woman. Based on the anti-VEGF mechanism of action for ranibizumab [see Clinical Pharmacology (12.1)], treatment with SUSVIMO (ranibizumab injection) may pose a risk to human embryofetal development.

All pregnancies have a background risk of birth defects, loss, and other adverse outcomes. The background risk of major birth defects and miscarriage for the indicated population is unknown. In the U.S. general population, the estimated background risk of major birth defects is 2% – 4% and of miscarriage is 15% – 20% of clinically recognized pregnancies.

Data

Animal Data

An embryo-fetal developmental toxicity study was performed on pregnant cynomolgus monkeys. Pregnant animals received intravitreal injections of ranibizumab every 14 days starting on Day 20 of gestation, until Day 62 at doses of 0, 0.125, and 1 mg/eye. Skeletal abnormalities including incomplete and/or irregular ossification of bones in the skull, vertebral column, and hindlimbs and shortened supernumerary ribs were seen at a low incidence in fetuses from animals treated with 1 mg/eye of ranibizumab. The 1 mg/eye dose resulted in trough serum ranibizumab levels up to 41 times higher than observed human Cmax levels of SUSVIMO (ranibizumab injection) after treatment of a single eye.

No skeletal abnormalities were seen at the lower dose of 0.125 mg/eye, a dose which resulted in trough exposures similar to single eye treatment with SUSVIMO (ranibizumab injection) in humans. No effect on the weight or structure of the placenta, maternal toxicity, or embryotoxicity was observed.

8.2 Lactation

Risk Summary

There are no data available on the presence of ranibizumab in human milk, the effects of ranibizumab on the breastfed infant or the effects of ranibizumab on milk production/excretion. Because many drugs are excreted in human milk, and because the potential for absorption and harm to infant growth and development exists, caution should be exercised when SUSVIMO is administered to a nursing woman.

The developmental and health benefits of breastfeeding should be considered along with the mother's clinical need for SUSVIMO (ranibizumab injection) and any potential adverse effects on the breastfed child from ranibizumab.

8.3 Females and Males of Reproductive Potential

Contraception

Females of reproductive potential should use effective contraception during treatment with SUSVIMO (ranibizumab injection) and for at least 12 months after the last dose of SUSVIMO (ranibizumab injection).

Infertility

No studies on the effects of ranibizumab on fertility have been conducted and it is not known whether ranibizumab can affect reproduction capacity. Based on the anti-VEGF mechanism of action for ranibizumab, treatment with SUSVIMO (ranibizumab injection) may pose a risk to reproductive capacity.

8.4 Pediatric Use

The safety and efficacy of SUSVIMO (ranibizumab injection) in pediatric patients have not been established.

8.5 Geriatric Use

In the Archway study, 90% (222 of 248) of the patients randomized to treatment with SUSVIMO were ≥ 65 years old and approximately 57% (141 of 248) were ≥ 75 years old. No notable difference in treatment effect or safety was seen with increasing age.

11 DESCRIPTION

Ranibizumab is a recombinant humanized IgG1 kappa isotype monoclonal antibody fragment for intraocular use. Ranibizumab binds to and inhibits the biologic activity of human vascular endothelial growth factor-A (VEGF-A). Ranibizumab, which lacks an Fc region, has a molecular weight of approximately 48 kilodaltons and is produced by an E. coli expression system in a nutrient medium containing the antibiotic tetracycline. Tetracycline is not detectable in the final product.

SUSVIMO (ranibizumab injection) is supplied as a sterile, clear to slightly opalescent, colorless to slightly brownish solution for intravitreal use via the SUSVIMO implant. Each single-dose vial contains 10 mg of ranibizumab, histidine HCl (0.1 mg), polysorbate 20 (0.01 mg), sucrose (8.2 mg), and Water for Injection, in 0.1 mL of solution with a pH of 5.5. The SUSVIMO implant is designed to contain approximately 0.02 mL (2 mg) of ranibizumab solution when filled. SUSVIMO does not contain an antimicrobial preservative.

12 CLINICAL PHARMACOLOGY

12.1 Mechanism of Action

Ranibizumab binds to the receptor binding site of multiple biologically active forms of VEGF-A, including VEGF110. VEGF-A has been shown to cause neovascularization and leakage in models of ocular angiogenesis and vascular occlusion and is thought to contribute to pathophysiology of neovascular AMD. The binding of ranibizumab to VEGF-A prevents the interaction of VEGF-A with its receptors (VEGFR1 and VEGFR2) on the surface of endothelial cells, reducing endothelial cell proliferation, vascular leakage, and new blood vessel formation.

12.3 Pharmacokinetics

The SUSVIMO implant provides a continuous release of ranibizumab where the release of ranibizumab into the vitreous decreases over time as the concentration in the implant decreases. The ranibizumab serum and aqueous humor concentrations with a SUSVIMO 24-week and 36-week treatment interval are maintained below the maximum and above the minimum concentrations experienced with monthly 0.5 mg intravitreal ranibizumab.

Distribution

Ranibizumab did not accumulate in serum when administered with refills every 24 weeks or every 36 weeks.

Following implant insertion of SUSVIMO in patients with AMD, the mean (±SD) maximum ranibizumab serum concentration (Cmax) was 0.48 (±0.17) ng/mL and median (range) time to maximum serum concentration (Tmax) was 26 (1 – 89) days. Following the initial fill and refill of SUSVIMO in patients, maximum serum concentrations of ranibizumab were below the ranibizumab concentration necessary to inhibit the biological activity of VEGF by 50%.

Elimination

Metabolism

The metabolism of SUSVIMO (ranibizumab injection) has not been studied. SUSVIMO (ranibizumab injection) is a monoclonal antibody fragment and antibodies are cleared principally by catabolism.

Excretion

The full excretion profile for ranibizumab following administration of SUSVIMO is unknown.

Specific Populations

Patients with renal impairment were included in the population pharmacokinetic analysis of SUSVIMO (ranibizumab injection). Across all indications, systemic clearance of ranibizumab was slightly lower in renally impaired patients but was not clinically significant. No clinically significant differences in the pharmacokinetics of ranibizumab were observed based on age in the patient population.

12.6 Immunogenicity

As with all therapeutic proteins, there is potential for immune response in patients treated with ranibizumab including SUSVIMO. The detection of an immune response is highly dependent on the sensitivity, specificity, and drug tolerance level of the assay. Additionally, the observed incidence of antibody positivity in an assay may be influenced by several factors including assay methodology, sample handling, timing of sample collection, concomitant medications, and underlying disease. For these reasons, comparison of the incidence of antibodies in the study described below with the incidence of antibodies in other studies or to other products may be misleading.

Prior to treatment with SUSVIMO, 2.1-3.6% of patients with AMD, DME, or DR tested positive for anti-ranibizumab antibodies. In patients with AMD, after the SUSVIMO implant insertion and treatment, 12% (29 of 247) patients tested positive for anti-ranibizumab antibodies. In patients with DME, after 4 doses of intravitreal ranibizumab, and SUSVIMO implant insertion and treatment, 13% (41 of 320) patients tested positive for anti-ranibizumab antibodies. In patients with DR, after 2 doses of intravitreal ranibizumab, and SUSVIMO implant insertion and treatment, 17% (17 of 99) patients tested positive for anti-ranibizumab antibodies. No clinically meaningful differences in the pharmacokinetics, efficacy, or safety in patients testing positive for anti-ranibizumab antibodies were observed.

13 NONCLINICAL TOXICOLOGY

13.1 Carcinogenesis, Mutagenesis, Impairment of Fertility

No studies have been conducted to determine the carcinogenic or mutagenic potential of SUSVIMO (ranibizumab injection). Based on the anti-VEGF mechanism of action for ranibizumab, treatment with SUSVIMO (ranibizumab injection) may pose a risk to reproductive capacity [see Females and Males of Reproductive Potential (8.3)].

14 CLINICAL STUDIES

14.1 Neovascular (wet) Age-related Macular Degeneration (AMD)

The clinical efficacy and safety of SUSVIMO (ranibizumab injection) was assessed in a randomized, visual assessor-masked, active treatment-controlled study (Archway-NCT03677934) in patients with AMD. A total of 415 patients (248 in the SUSVIMO arm and 167 in the intravitreal ranibizumab arm) were enrolled and treated in this study. Patients were diagnosed with AMD within the 9 months prior to screening and received ≥ 3 doses of anti-VEGF intravitreal agents in the study eye within the last 6 months prior to screening. Each patient was required to have demonstrated a response to an anti-VEGF intravitreal agent prior to randomization. Patients were randomized in a 3:2 ratio to receive continuous delivery of SUSVIMO (ranibizumab injection) via the SUSVIMO implant every 24 weeks or 0.5 mg intravitreal ranibizumab injections every 4 weeks. For patients randomized to the SUSVIMO arm, supplemental treatment with 0.5 mg intravitreal ranibizumab injections was available at Weeks 16, 20, 40, 44, 64, 68, 88, and 92, if needed. In the first 24 weeks, 1.6% of patients assessed for supplemental treatment received 1 or more supplemental treatment(s) and in the following 24 weeks, 5.4% of patients assessed for supplemental treatment received 1 or more supplemental treatment(s).

The primary efficacy endpoint of change from baseline in distance Best Corrected Visual Acuity (BCVA) score averaged over Week 36 and Week 40 demonstrated that SUSVIMO was equivalent to intravitreal ranibizumab injections administered every 4 weeks. Detailed efficacy results are shown in Table 3 and Figure 29 below.

Table 3 Visual Acuity outcomes at Week 40 in Archway (GR40548) Study
Outcome Measure [BCVA measured using the Early Treatment Diabetic Retinopathy Study (ETDRS) visual acuity chart at a starting distance of 4 meters.] | SUSVIMO (100 mg/mL) n=248 | Intravitreal ranibizumab 0.5 mg (10 mg/mL) n=167 | Difference (95% CI) [All estimates are adjusted estimates based on a mixed-effect model with repeated measures. SUSVIMO arm - intravitreal ranibizumab arm. 95% is a rounding of 95.03% CI; The type 1 error was adjusted for interim safety monitoring.]
Adjusted Mean change from baseline in BCVA score averaged over Weeks 36 and 40 | 0.2 | 0.5 | -0.3 (-1.7, 1.1) [Equivalence margins were ±4.5 letters.]
BCVA = Best corrected visual acuity

Figure 29 Adjusted Mean change from Baseline in Best Corrected Visual Acuity in study eye through Week 48 in the Archway (GR40548) study [Prior to study treatment, a median of 4 doses of anti-VEGF intravitreal agents were administered in the study eye of patients in the SUSVIMO and intravitreal ranibizumab arms.] , [Decrease in BCVA at Week 4 during post-operative recovery period.]

Q24W = every 24 weeks; Q4W = every 4 weeks

Consistent results were observed across patient subgroup analyses for mean change from baseline in BCVA score (age, gender, number of prior anti-VEGF intravitreal injections, and baseline BCVA score).

14.2 Diabetic Macular Edema (DME)

The clinical efficacy and safety of SUSVIMO were assessed in a randomized, visual assessor-masked, active treatment-controlled study (Pagoda-NCT04108156) in patients with DME. A total of 634 patients (381 in the SUSVIMO arm and 253 in the intravitreal ranibizumab 0.5 mg arm) were enrolled and treated in this study. Patients were randomized in a 3:2 ratio to receive continuous delivery of SUSVIMO via the implant every 24 weeks or 0.5 mg intravitreal ranibizumab injections every 4 weeks.

Prior to study treatment, a median of 4 doses of intravitreal ranibizumab 0.5 mg were administered in the study eye of patients in the SUSVIMO and intravitreal ranibizumab arms. Patient ages ranged from 29 to 89 years with a mean of 60.7 years. A total of 21% of patients were previously treated for DME. At baseline, the overall mean visual acuity was 65.3 letters (range: 25 to 89 letters).

The primary efficacy endpoint of change from baseline in distance Best Corrected Visual Acuity (BCVA) score averaged over Week 60 and Week 64 demonstrated that SUSVIMO was non-inferior to intravitreal ranibizumab injections administered every 4 weeks. Detailed efficacy results are shown in Table 4 and Figure 30 below.

Table 4 Key efficacy outcomes at Week 60 and Week 64 in the Pagoda (GR40550) Study
Outcome Measure [BCVA measured using the Early Treatment Diabetic Retinopathy Study (ETDRS) visual acuity chart at a starting distance of 4 meters.] | SUSVIMO 100 mg/mL n=381 | Intravitreal ranibizumab 0.5 mg (10 mg/mL) n=253 | Difference (95% CI) [All estimates are adjusted estimates based on a mixed-effect model with repeated measures. 95% is a rounding of 95.05% CI; The type 1 error was adjusted for interim safety monitoring.]
Change in BCVA scores from baseline averaged over Week 60 and Week 64 Adjusted Mean | 9.6 | 9.4 | 0.2 (-1.2, 1.6)
BCVA = Best corrected visual acuity

Figure 30 Adjusted Mean change from Baseline in Best Corrected Visual Acuity in study eye through Week 64 in the Pagoda (GR40550) study

Consistent results were observed across patient subgroup analyses for mean change from baseline in BCVA score (age, ethnicity, gender, baseline HbA1c score, focal/macular laser history, baseline BCVA score, prior intravitreal anti-VEGF treatment and DR severity).

14.3 Diabetic Retinopathy (DR)

The clinical efficacy and safety of SUSVIMO were assessed in a randomized, visual assessor and reading center-masked study (Pavilion-NCT04503551) in patients with moderately-severe to severe non-proliferative diabetic retinopathy (NPDR) [Early Treatment Diabetic Retinopathy Study Diabetic Retinopathy Severity Scale (ETDRS-DRSS) of 47 or 53], without center-involved DME (CI-DME), and who had not received prior treatment in the study eye for DR. A total of 174 patients (106 in the SUSVIMO arm and 68 in the observational comparator arm) were enrolled in this study.

Patients who had not received prior treatment in the study eye for DR were randomized in a 5:3 ratio to continuous delivery of SUSVIMO via the implant every 36 weeks or to clinical observation. Prior to the implant procedure, two loading doses of intravitreal ranibizumab 0.5 mg were administered in the study eye. The observational comparator arm did not receive loading doses of intravitreal ranibizumab. For patients who developed CI-DME or proliferative diabetic retinopathy/anterior segment neovascularization in either arm, supplemental treatment with intravitreal injections of 0.5 mg ranibizumab was available per investigator's clinical judgment at any non-refill-exchange study visit. Patient ages ranged from 24 to 83 years with a mean of 53.9 years. At baseline, the overall mean visual acuity was 82.4 letters (range: 69 to 97 letters).

The primary efficacy endpoint was the proportion of patients with a ≥ 2-step improvement on the ETDRS-DRSS from baseline at Week 52 versus clinical observation. SUSVIMO with two loading doses of intravitreal ranibizumab was superior to clinical observation at Week 52. Detailed results are shown in Table 5 and Figure 31 below.

Table 5 Efficacy Outcomes through Week 52 in the Pavilion (GR41675) Study
Outcome Measure | SUSVIMO 100 mg/mL (n=106) | Clinical Observation (n=68) | Difference 95% CI [All estimates are adjusted estimates based on the CMH method. 95% is a rounding of 95.04% CI; the type 1 error was adjusted for interim safety monitoring. p<0.01 compared with clinical observation.]
Adjusted proportion of patients with ≥ 2-step improvement from baseline on the ETDRS-DRSS at Week 52 | 80% | 9% | 71% (61%, 81%)
ETDRS-DRSS = Early Treatment Diabetic Retinopathy Study Diabetic Retinopathy Severity Scores
CMH = Cochran-Mantel-Haenszel test

Figure 31 Adjusted Proportion of Patients with a ≥ 2-Step Improvement from Baseline on ETDRS-DRSS in Study Eye over Time through Week 52 in the Pavilion (GR41675) Study

In the SUSVIMO arm, none of the patients assessed for supplemental treatment received any supplemental injections of intravitreal ranibizumab and 40% of patients in the observational comparator arm received 1 or more supplemental treatments through Week 52.

Consistent results were observed across patient subgroup analyses for ETDRS-DRSS score including age, race, ethnicity, baseline hemoglobin (HbA1c) and baseline ETDRS-DRSS score.

16 HOW SUPPLIED/STORAGE AND HANDLING

16.1 How Supplied

Each SUSVIMO initial fill needle kit (NDC 50242-078-55) contains:

- One SUSVIMO 100 mg/mL single-dose glass vial
- One SUSVIMO initial fill needle (34-gauge needle with a 5 μm integrated filter) with a blue cap

Each SUSVIMO (ranibizumab injection) carton (NDC 50242-078-12) contains one SUSVIMO (ranibizumab injection) 100 mg/mL that is clear to slightly opalescent, colorless to slightly brownish solution in a single-dose glass vial.

Each SUSVIMO initial fill needle carton contains a SUSVIMO initial fill needle (34-gauge needle with a 5 μm integrated filter) with a blue cap.

Each SUSVIMO refill needle carton contains a SUSVIMO refill needle (34-gauge vented needle with a 5 μm integrated filter) with a clear cap.

Device and Materials Description

Components

Figure 32

SUSVIMO implant

- SUSVIMO implant (Figure 33) is capable of holding 0.02 mL of drug, and is secured within the sclera, by the extrascleral flange that remains visible through the conjunctiva following insertion.
- The septum is a self-sealing interface through which ranibizumab is administered to fill the implant.

Figure 33

SUSVIMO (ranibizumab injection) 100 mg/mL vial

- SUSVIMO (ranibizumab injection) (Figure 34) is used to fill the implant with ranibizumab prior to insertion or during subsequent refill-exchange in an office-based setting.

Figure 34

SUSVIMO refill needle

- SUSVIMO refill needle (Figure 35) consists of a 34 G vented needle assembly, silicone soft stop, and a 5 μm integrated filter within the needle hub. It is designed to simultaneously exchange the contents of the implant reservoir with replacement ranibizumab in an office-based setting. As replacement ranibizumab is administered into the implant through the stainless-steel cannula, fluid remaining in the implant flows through openings in the vented needle and is collected in the fluid collection reservoir.
- SUSVIMO refill needle is distinguished by its clear cap.

Figure 35

Materials List

Materials that are required and supplied to perform the procedure are:

- SUSVIMO refill needle, 34 G, with clear cap
- SUSVIMO (ranibizumab injection) 100 mg/mL

Additional materials required to perform the procedure but are not provided are:

- One sterile 1 mL Luer Lock syringe (not included)
- One sterile 5-micron filter needle (19-gauge × 1½ inch) (not included)
- Anesthetic ophthalmic solutions
- Ophthalmic broad-spectrum microbicide solution
- Cotton tips and gauze
- Sterile powder free gloves
- Face masks
- Lid speculum
- Magnification such as visor or loupes
- Task lighting
- Indirect ophthalmoscope and lens
- Sterile drape (optional for refill-exchange procedure)

16.2 Storage

Store SUSVIMO initial fill needle kit at 2°C to 8°C (36°F to 46°F). Do not freeze. Protect from light. Do not shake. The SUSVIMO initial fill needle has been sterilized with electron beam processing.

Store SUSVIMO (ranibizumab injection) 100 mg/ mL vial at 2°C to 8°C (36°F to 46°F). Do not freeze. Protect from light. Do not shake. Prior to use, the unopened vial may be kept at 9°C to 30°C (48°F to 86°F) for up to 24 hours provided it is protected from light.

Store the SUSVIMO implant and insertion tool assembly, refill needle and explant tool at room temperature 15°C to 25°C (59°F to 77°F). The SUSVIMO implant and insertion tool assembly has been sterilized with ethylene oxide gas. The SUSVIMO refill needle and explant tool has been sterilized with electron beam processing.

Store the SUSVIMO initial fill needle at 2°C to 25°C (36°F to 77°F). The SUSVIMO initial fill needle has been sterilized with electron beam processing.

16.3 Handling

SUSVIMO components are supplied sterile and are for single-use only. Do not reprocess, re-sterilize, or reuse SUSVIMO components. Do not use if the sterility has been compromised or the contents have been dropped, damaged or tampered with. Do not use past the expiration date printed on the label. Do not open sealed tray until time of use. Avoid contact between sharp surgical instruments and the SUSVIMO implant as the material of the septum and silicone encasing is soft and susceptible to damage.

Important Device Handling Information

- Use caution when performing ophthalmic procedures (e.g., B-scan ophthalmic ultrasound, scleral depression, or gonioscopy) that may cause deflection or movement of the implant and subsequent injury.

Ocular Implant Initial Fill Procedure

- Minimize air bubbles within the implant reservoir as they may cause slower drug release. If an air bubble is present, it must be no larger than 1/3 of the widest diameter of the implant. If excess air is observed after initial fill, do not use the implant.

Ocular Implant Insertion Procedure

- Perpendicular entry of the implant is important to avoid contact between the implant and intraocular structures such as the lens, as contact between the implant and the intraocular structures may cause adverse reactions such as traumatic cataract.
- Avoid excessive force on the globe by first ensuring that the tip of the implant has passed through the sclero-pars plana incision before slowly pushing the implant into place.

Ocular Implant Removal Procedure

- Do not grasp the implant by the short axis of the implant flange. Remove the implant in a gentle manner. Perpendicular exit of the implant is important to avoid contact between the implant and intraocular structures such as the lens.

17 PATIENT COUNSELING INFORMATION

Advise the patient to read the FDA-approved patient labeling (Medication Guide).

Advise patients on the following after the implant insertion procedure:

Positioning:

- Keep head above shoulder level for the rest of the day.
- Sleep with head on 3 or more pillows during the day and the night after surgery.

How to care for the treated eye after the procedure:

- Do not remove the eye shield until they are instructed to do so by their healthcare provider. At bedtime, continue to wear the eye shield for at least 7 nights following the implant surgery.
- Administer all post-operative eye medications as directed by their healthcare provider.
- Do not push on the eye, rub the eye, or touch the area of the eye where the implant is located (underneath the eyelid in the upper and outer part of the eye) for 30 days following the implant insertion.
- Do not participate in strenuous activities until 1-month after the implant insertion or after discussion with their healthcare provider.

Magnetic Resonance (MR) Conditional information:

- The SUSVIMO implant is MR conditional. Inform their healthcare provider that they have SUSVIMO implanted in their eye and show their healthcare provider the SUSVIMO implant card should they require Magnetic resonance imaging (MRI).

Advise patients on the following after the Refill-Exchange procedure:

- Refrain from pushing on the treated eye, rubbing the eye, or touching the eye in the area of the implant (located underneath the eyelid in the upper and outer part of your eye) for 7 days following the refill-exchange procedure.
- Administer eye drops as directed by their healthcare provider.

Advise patients on the following after the implant removal procedure (if it is deemed medically necessary):

- Keep your head above shoulder level for the rest of the day.
- Sleep with your head on 3 or more pillows if lying down during the day and night after the implant removal.
- Wear an eye shield for at least 7 nights following the implant removal.
- Do not participate in strenuous activities until 14 days following the implant removal.
- Administer all post-operative anti-inflammatory and antimicrobial drops, as directed by your healthcare provider.

Advise patients on the following throughout SUSVIMO treatment:

- Do not drive or use machinery until the eye shield can be removed and visual function has recovered sufficiently [see Adverse Reactions (6.1)].
- The SUSVIMO implant and/or implant related procedures have been associated with conjunctival reactions (bleb, erosion, retraction), vitreous hemorrhage, endophthalmitis, rhegmatogenous retinal detachment, the dislocation of the implant, septum dislodgement, and a temporary decrease in vision.
- While the implant is in the eye, avoid rubbing the eye or touching the area as much as possible. However, if necessary to do so, make sure hands are cleaned prior to touching the eye.
- Seek immediate care from an ophthalmologist if there are sudden changes in their vision (an increase in moving spots, the appearance of "spider webs", flashing lights, or a loss in vision), increasing eye pain, progressive vision loss, sensitivity to light, redness in the white of the eye, a sudden sensation that something is in their eye, or eye discharge or watering [see Warnings and Precautions (5)].

SUSVIMO® [ranibizumab injection]
Manufactured by:
Genentech, Inc.
A Member of the Roche Group
1 DNA Way
South San Francisco, CA 94080-4990
U.S. License No.: 1048

SUSVIMO is a registered trademark of Genentech, Inc.
©2025 Genentech, Inc.

MEDICATION GUIDE
SUSVIMO® (suss-VIH-moh)
(ranibizumab injection)
for intravitreal use via SUSVIMO ocular implant

What is the most important information I should know about SUSVIMO?
SUSVIMO (ranibizumab injection) is delivered into the eye using the SUSVIMO implant. The SUSVIMO implant and the procedures to insert, fill, refill and remove the eye (ocular) implant can cause serious side effects including:

- an eye infection (endophthalmitis). Endophthalmitis is an infection of the eyeball that can cause permanent damage to your eye including blindness. Call your healthcare provider right away if you have increasing eye pain, vision loss, sensitivity to light, or redness in the white of the eye. Endophthalmitis requires urgent (same day) medical or surgical treatment.
- a missing layer on top of the white part of the eye (conjunctival erosion). Conjunctival erosion is an area that becomes missing (defect) in the layer (conjunctiva) that covers the white part of the eye which may result in exposure of the implant. Call your healthcare provider right away if you have a sudden feeling that something is in your eye, if you have eye discharge, or watering of the eye. Conjunctival erosion may require surgical treatment.
- an opening of the layer that covers the white part of the eye (conjunctival retraction). Conjunctival retraction is an opening or gaping in the layer (conjunctiva) that covers the white part of the eye which may cause the implant to be exposed. Call your healthcare provider right away if you have a sudden feeling that something is in your eye, if you have eye discharge, or watering of the eye. Conjunctival retraction may require surgical treatment.

See "What are the possible side effects of SUSVIMO?" for other serious side effects that may happen while in treatment with SUSVIMO.
To help prevent or keep these side effects from becoming more serious follow all post-procedure instructions your healthcare provider gives you. See "How will I receive SUSVIMO?".

What is SUSVIMO?
SUSVIMO (ranibizumab injection) is a prescription medicine used to treat adults with:

- Neovascular (wet) Age-related Macular Degeneration (AMD) who have responded to at least two injections of a Vascular Endothelial Growth Factor (VEGF) inhibitor in the gel-like part of the eye (intravitreal).
- Diabetic Macular Edema (DME) who have responded to at least two injections of a Vascular Endothelial Growth Factor (VEGF) inhibitor in the gel-like part of the eye (intravitreal).
- Diabetic Retinopathy (DR) who have responded to at least two injections of a Vascular Endothelial Growth Factor (VEGF) inhibitor in the gel-like part of the eye (intravitreal).

It is not known if SUSVIMO is safe and effective in children.

Do not receive SUSVIMO if you:

- have an infection in or around your eye.
- have active swelling around your eye that may include pain and redness.
- are allergic to ranibizumab or any of the ingredients in SUSVIMO. See the end of this Medication Guide for a complete list of ingredients in SUSVIMO.

Talk to your healthcare provider before receiving this SUSVIMO if you have any of these conditions.

Before receiving SUSVIMO, tell your healthcare provider about all of your medical conditions, including if you:

- are currently taking or have recently taken medicines that lower the chance of blood clots forming in the body such as warfarin, low or regular doses of aspirin, or nonsteroidal anti-inflammatory drugs (NSAID).
- are pregnant or plan to become pregnant. It is not known if SUSVIMO will harm your unborn baby. You should use birth control during your treatment with SUSVIMO and for 12 months after your last dose of SUSVIMO.
- are breastfeeding or plan to breastfeed. It is not known if SUSVIMO passes into your breast milk. Talk to your healthcare provider about the best way to feed your baby if you receive SUSVIMO.

Tell your healthcare provider about all the medicines you take, including prescription and over-the-counter medicines, vitamins, and herbal supplements.

How will I receive SUSVIMO?

- SUSVIMO is implanted through the white part of the eye (sclera) by your healthcare provider.
- Your healthcare provider will refill your implant device every 6 months (about every 24 weeks) if you have AMD or DME or every 9 months (about every 36 weeks) if you have DR.
- If you miss a scheduled refill, call your healthcare provider as soon as possible to reschedule your refill. Your next refill should be given 6 months after your last refill if you have AMD or DME, or 9 months after your last refill if you have DR.

Your healthcare provider will give you instructions to follow after the implant insertion, the refill procedure, and the implant removal. The instructions may include:
After the Implant Insertion:

- Positioning of your head
  - Keep your head above shoulder level for the rest of the day.
  - Sleep with your head on 3 or more pillows during the day and night after your implant insertion.
- How to care for your eye
  - Do not remove the eye shield from your eye until you are told to by your healthcare provider. At bedtime, continue to wear an eye shield for at least 7 nights following the implant insertion.
  - Take all post-operative eye medicines as your healthcare provider tells you to.
  - Do not push on the eye, rub the eye, or touch the area of the eye where the implant is located (underneath the eyelid in the upper and outer part of your eye) for 30 days following the implant insertion.
  - Do not participate in strenuous activities until 1 month after the implant insertion or after talking to your healthcare provider.
- Magnetic Resonance Imaging (MRI) Implant Card
  - Get your implant card from your healthcare provider after receiving the implant and keep the card in a safe place for future reference. The implant card contains important information about your SUSVIMO implant.
  - Show your current and future healthcare providers your implant card. This is important if you need to have an MRI. You may only receive an MRI under very specific conditions if you have the SUSVIMO implant. Your healthcare provider will review the information on the implant card and will let you know if you should receive an MRI.

After the Refill Procedure:

- Do not push on the eye, rub the eye, or touch the area of the eye where the implant is located (underneath the eyelid in the upper and outer part of your eye) for 7 days following the refill procedure.
- Take eye drops exactly as your healthcare provider tells you to take them.

After the Implant Removal:

- Keep your head above shoulder level for the rest of the day.
- Sleep with your head on 3 or more pillows if lying down during the day and night after implant removal.
- Wear an eye shield for at least 7 nights following the implant removal.
- Do not participate in strenuous activities until 14 days following the implant removal.
- Give all post-operative drops, as told by your healthcare provider.

These are not all the instructions you may receive from your healthcare provider. Following all post-procedure instructions may help prevent serious side effects or keep side effects from becoming more serious. See "What is the most important information I should know about SUSVIMO?".

What should I avoid while receiving SUSVIMO?

- Do not drive or use machinery until the eye shield can be removed and you can see.
- Avoid rubbing your eye or touching the area of your eye where the implant is located as much as possible while the implant is in place. If you have to rub or touch your eye, wash your hands first.

What are the possible side effects of SUSVIMO?
See "What is the most important information I should know about SUSVIMO?" on the first page.
In addition to those side effects listed on page one, the SUSVIMO implant and the procedures to insert, fill, refill and remove the eye (ocular) implant can cause other serious side effects including:

- Tear and separation of layers of the retina (Rhegmatogenous retinal detachment). Rhegmatogenous retinal detachment is a tear and separation of one of the layers of the retina in the back of the eye that senses light. Call your healthcare provider or go to the emergency room right away if you see flashing lights, see a curtain or veil covering part of your vision, have a change in your vision, or a loss of vision. Rhegmatogenous retinal detachment requires surgical treatment.
- Implant movement (Implant dislocation): Tell your healthcare provider right away if you notice that the implant has moved out of place. This movement may require surgical treatment to correct.
- Implant damage: Damage to the implant that prevents continued treatment (refills) with SUSVIMO. If the implant is not able to be properly refilled, your wet AMD may be inadequately treated and your physician may remove the implant and/or change your treatment.
- Bleeding (Vitreous hemorrhage): Vitreous hemorrhage is bleeding within the gel-like substance (vitreous) inside of your eye. Call your healthcare provider right away if you have an increase in moving spots or what looks like spider webs in your vision as you may need an additional eye surgery.
- Bump on top of the white layer of the eye (Conjunctival bleb): Conjunctival bleb is a small bulge in the layer (conjunctiva) that covers the white part of the eye where the implant is inserted. This may be due to leakage of fluid from the inside of the eye. Call your healthcare provider right away if you have a sudden feeling that something is in your eye (foreign body sensation), see a bulge over the white part of your eye, if you have eye discharge, or watering in the eye. You may need medical or surgical treatment.
- Temporary decrease in vision after the SUSVIMO procedure.

The most common side effects of SUSVIMO include:

- blood on the white of the eye
- eye pain

- redness in the white of the eye
- sensitivity to light

These are not all the possible side effects of SUSVIMO.
Call your doctor for medical advice about side effects. You may report side effects to FDA at 1-800-FDA-1088.
You may also report side effects to Genentech at 1-888-835-2555.

General information about the safe and effective use of SUSVIMO.
Medicines are sometimes prescribed for purposes other than those listed in a Medication Guide. You can ask your pharmacist or healthcare provider for information about SUSVIMO that is written for health professionals.

What are the ingredients in SUSVIMO (ranibizumab injection)?
Active ingredient: ranibizumab
Inactive ingredients: histidine HCl, polysorbate 20, sucrose.
Manufactured by: Genentech, Inc., A Member of the Roche Group, 1 DNA Way, South San Francisco, CA 94080-4990
U.S. License No.: 1048

This Medication Guide has been approved by the U.S. Food and Drug Administration

Revised: 5/2025

INSTRUCTIONS FOR USE

Susvimo®
(ranibizumab injection)
For Susvimo ocular implant use
Instructions for Use

Initial Fill and Implant Procedure

Caution: Federal Law (USA) restricts this device to sale by or on the order of a physician.

Susvimo procedures should be performed by an ophthalmologist experienced in vitreoretinal surgery.

Refer to the Susvimo (ranibizumab injection) 100 mg/mL prescribing information for a complete list of indications, contraindications, warnings, precautions, and adverse events.

Contents

Introduction

3 | Device Description
4 | Components
8 | Intended Use/Indications for Use
8 | Contraindications
8 | Warnings
9 | Precautions
10 | How Supplied, Handling, and Storage

Instructions for Use

11 | Introduction and Materials
13 | Preparatory Procedures
14 | Infusion Line Placement Procedure
15 | Conjunctival Dissection Procedure
17 | Syringe Preparation and Initial Implant Fill
25 | Implant Insertion
35 | Disposal and Post-insertion Procedures
36 | Explanation of symbols on product or package labeling

Introduction

These instructions include only the procedure for filling and inserting the Susvimo implant. For more information, refer to the Susvimo prescribing information for the refill-exchange procedure and Susvimo Instructions for Use for the implant removal procedure.

Device Description

Susvimo is an intraocular drug delivery system designed to be used specifically with Susvimo (ranibizumab injection) 100 mg/mL. The system consists of an intraocular implant along with ancillary devices used to fill, insert, and explant (if needed) the implant.

The implant is a refillable drug reservoir that is inserted into the eye through the pars plana. The implant is secured within the scleral incision, with the extrascleral flange that remains visible through the conjunctiva following insertion. Once filled with ranibizumab, the implant is designed to provide continuous release of ranibizumab. The implant will be refilled with ranibizumab in an office-based setting via an administration through the conjunctiva and implant septum.

Components

Figure 1

Susvimo components for initial fill and implant procedure

Susvimo implant (packaged with insertion tool assembly)

Susvimo implant (Figure 2 and Figure 3) is a refillable reservoir inserted into the eye through the pars plana. The body of the implant, which includes the release control element, extends into the vitreous cavity.

Figure 2
Susvimo implant

Figure 3
Susvimo implant detail

Table 1 Susvimo implant component description
Implant components | Description
Extrascleral flange | The extrascleral flange provides secure anchoring of the implant within the scleral incision and is encased in silicone.
Septum | The septum is a self-sealing interface through which ranibizumab is administered into the implant both prior to insertion and during subsequent refills in an office-based setting.
Body | The body of the implant contains a hollow drug reservoir, capable of holding 0.02 mL of drug.
Release control element | The titanium release control element controls the rate of ranibizumab diffusion from the drug reservoir into the vitreous.

Susvimo insertion tool assembly

Susvimo insertion tool assembly is designed to facilitate handling of the implant during the initial fill and implant procedure. The insertion tool assembly is comprised of a carrier and handle (Figure 4 and Figure 5), described in more detail below:

Figure 4
Susvimo insertion tool carrier

Figure 5
Susvimo insertion tool handle

Table 2 Susvimo insertion tool assembly component description
Insertion tool assembly components | Description
Gripper tips | The implant is provided pre-positioned in the insertion tool assembly gripper tips. After initial fill of the implant with ranibizumab, the implant and gripper tips are transferred from the insertion tool carrier to the insertion tool handle.
Luer lock slot | The syringe is loaded into the insertion tool carrier by aligning the syringe Luer lock with the insertion tool carrier Luer lock slot.
Guide channel | The guide channel serves to direct the syringe and initial fill needle in the insertion tool carrier during the initial fill of the implant.
Release button | Pressing the release button on the insertion tool handle will open the gripper tips and release the implant.

Susvimo (ranibizumab injection) 100 mg/mL vial

Susvimo (ranibizumab injection) (Figure 6) is used to fill the implant prior to insertion or during subsequent refill-exchange in an office-based setting.

Figure 6
Susvimo (ranibizumab injection) 100 mg/mL vial

Susvimo initial fill needle

Susvimo initial fill needle (Figure 7) is designed to fill the implant with ranibizumab prior to implant insertion. The initial fill needle is distinguished by its blue cap.

Figure 7
Susvimo initial fill needle

Table 3 Susvimo initial fill needle component description
Initial fill needle components | Description
Needle | 34 G needle
Integrated filter | Integrated 5 µm filter within needle hub

Intended Use/Indications for Use

Susvimo ocular implant is approved for use with Susvimo (ranibizumab injection). Refer to the Susvimo (ranibizumab injection) prescribing information for a complete list of indications, contraindications, warnings, precautions, and adverse events.

Contraindications

Susvimo is contraindicated in patients with ocular or periocular infections, with active intraocular inflammation, or with known hypersensitivity to ranibizumab or any of the excipients in Susvimo (ranibizumab injection) 100 mg/mL. Hypersensitivity reactions may manifest as severe intraocular inflammation.

Warnings

- Do not use if the sterility has been compromised or the contents have been dropped, damaged or tampered with.
- Minimize air bubbles within the implant reservoir as they may cause slower drug release. If an air bubble is present, it must be no larger than 1/3 of the widest diameter of the implant.
  If excess air is observed after initial fill, do not use the implant.
- Perpendicular entry of the implant is important to avoid contact between the implant and intraocular structures such as the lens, as contact between the implant and the intraocular structures may cause adverse events such as traumatic cataract.
- Avoid excessive force on the globe by first ensuring that the tip of the implant has passed through the sclero-pars plana incision before slowly pushing the implant into place.

Precautions

- Read and follow all instructions, warnings, and cautions prior to use.
- Susvimo procedures should be performed by an ophthalmologist experienced in vitreoretinal surgery.
- Use the Susvimo components and materials as specified in these instructions to perform the implant insertion procedure including initial fill.
- Avoid contact between sharp surgical instruments and the implant as the material of the septum and silicone encasing are soft and susceptible to damage.
- The implant is MR Conditional. The Patient Implant card is provided with instructions and must be completed and given to the patient after implant insertion. For further information please refer to the 'Post-insertion patient instructions' section.

Use with Standard Procedures

Susvimo implant is compatible for use with the following standard procedures: A-scan ophthalmic ultrasound, slit lamp examination, indirect ophthalmoscopy, tonometry, optical coherence tomography (OCT), visual field (perimetry), standard lasers for ophthalmic treatments, radiography (x-ray), computed tomography (CT) scan, fluorescein/ indocyanine angiography, and fundus autofluorescence.

Use caution when performing ophthalmic procedures that may cause deflection of the implant and subsequent injury. For example, B-scan ophthalmic ultrasound, scleral depression, or gonioscopy.

Magnetic Resonance Imaging (MRI) Safety Information

MR Conditional.

Non-clinical testing has demonstrated that the Susvimo implant is MR Conditional. A patient with this device can be safely scanned in an MR system meeting the following conditions:

- Static magnetic field of 1.5-Tesla (1.5 T) or 3-Tesla (3 T)
- Maximum spatial field gradient of 3,000 G/cm (30 T/m)
- Maximum MR system reported, whole body averaged specific absorption rate (SAR) of 4.0 W/kg (First Level Controlled Operating Mode)

Under the scan conditions defined above, the Susvimo implant is expected to produce a maximum temperature rise of less than 1°C after 15 minutes of continuous scanning.

In non-clinical testing, the image artifact caused by the device extends approximately 4 mm from the Susvimo implant when imaged with a gradient echo pulse sequence in a 3 T MRI system.

How Supplied, Handling, and Storage

- All Susvimo components are supplied sterile.
  Do not reprocess or resterilize.
- All Susvimo components are for single use only.
  Do not reuse Susvimo components.
- Do not open sealed tray until time of use.
- Do not use if the package is damaged or broken as sterility may be compromised.
- Do not use past the expiration date printed on the label.

Susvimo ocular implant and insertion tool assembly

- The sealed tray has been sterilized with ethylene oxide gas.
- Store the Susvimo implant and insertion tool assembly at room temperature 15°C to 25°C (59°F to 77°F).

Susvimo (ranibizumab injection)

- Susvimo should be stored at 2°C to 8°C (36°F to 46°F). Do not freeze. Protect from light. Do not shake. Prior to use, the unopened vial may be kept at 9°C to 30°C (48°F to 86°F) for up to 24 hours.

Initial fill needle

- Susvimo initial fill needle should be stored at 2°C to 25°C (36°F to 77°F). Susvimo initial fill needle has been sterilized with electron beam processing.

See Susvimo (ranibizumab injection) prescribing information for additional information.

Instructions for Use

Introduction and Materials

Implant insertion is a surgical procedure that is performed in an operating room. The implant is filled with Susvimo (ranibizumab injection) immediately prior to insertion.

Materials List

The materials that are required in the operating room on the day of the procedure are listed in Tables 4 and 5.

Table 4 Susvimo components provided for initial fill and implant procedure

Item Description

Susvimo ocular implant with insertion tool assembly

Susvimo initial fill needle, 34 G, with blue cap

Susvimo (ranibizumab injection) 100 mg/mL

Susvimo explant tool
(Refer to Susvimo implant removal Instructions for Use for information on implant removal.)

Table 5 Additional materials required but not provided for initial fill and implant procedure

Item Description

One sterile 1 mL Luer Lock syringe (not included)

One sterile 5-micron filter needle (19-gauge × 1½ inch) (not included)

Surgical microscope

Vitrectomy surgical control system

Standard 25 G or 27 G vitrectomy set up

23 G or 25 G 532 nm Endolaser probe and associated source

Standard vitrectomy tray (including adjustable caliper, 0.12 straight toothed forceps, blunt wescott scissors)

Cauterization equipment (including standard fine tip diathermy and eraser tip wet-field cautery)

Ophthalmic broad-spectrum microbicide solution

Marking pad

3.5 mm and 4.0 mm fixed caliper or equivalent fixed tool

3.5 mm fixed width gauge or equivalent fixed tool

19 G or 20 G MVR Straight Knife

Slit Knife, 3.2 mm Straight

Gut or Vicryl sutures for conjunctival tissues (suggested 7-0 to 9-0: monofilament recommended)

Indirect ophthalmoscope and lens

Drapes

Preparatory Procedures

1. Inspect packaging and components

- Prior to use in the operating room, inspect the packaging of the components for damage.
- Check the expiration date printed on the label.
- Remove the vial from the carton.
  NOTE: the outside of the vial is not sterile.
- Open sterile packaging and using aseptic technique, remove the components from their tray.
- Inspect components and place onto sterile field (Figure 8).

Warning
Do not use if the sterility has been compromised or the contents have been dropped, damaged, or tampered with.

Figure 8
Susvimo components on sterile field

2. Inspect Susvimo (ranibizumab injection)

- Visually inspect the contents of the ranibizumab vial for particulate matter and discoloration.
- The drug solution should be colorless to slightly brownish.

Caution
Do not use if particulate, cloudiness or discoloration are visible.

3. Patient Preparation

- Dilate the pupil of the eye.
- Place the patient in a supine position on the operating table.
- Implant insertion is a surgical procedure and therefore requires sterile controls (i.e. use of broad-spectrum microbicide solution on eye including lids and lashes and draping) be in place to minimize the risk of ocular infection.
- Perform the procedure under local anesthesia using either peribulbar, retrobulbar, or sub-Tenon's technique.
- Place lid speculum.

Infusion Line Placement Procedure

1. Place infusion line

- Place an infusion cannula in the inferotemporal quadrant via an angled entry wound.
  - Alternate placement is acceptable based on patient anatomy per physician discretion (superotemporal placement should be avoided).
  - Alternatively, the line may be placed after the peritomy but prior to the scleral dissection.
- Attach the infusion line. Keep the infusion line off (Figure 9).

Figure 9
Place infusion cannula in inferotemporal quadrant

Conjunctival Dissection Procedure

1. Identify the site of insertion; - Identify the site in the superotemporal quadrant 4 mm posterior to the limbus where the implant will be inserted (Figure 10 and Figure 11). - Placing a traction suture is strongly recommended for better visualization of the superotemporal quadrant throughout the entire implant insertion procedure. | Figure 10 Superotemporal quadrant Figure 11 4 mm posterior to the limbus
2. Create conjunctival peritomy
Caution
The peritomy size should be at least 6 mm by 6 mm centered around the selected implant location to ensure the proper clearance of the conjunctiva and Tenon's capsule from the implant flange once the implant is inserted into the eye.
- Measure with adjustable caliper and create at least a 6mm by 6mm peritomy of the conjunctiva and Tenon's capsule around the selected implant location, using wet field cautery (eraser tip) to achieve hemostasis of the underlying episcleral tissues (Figure 12). - A peritomy size of at least 6 mm by 6 mm centered around the selected implant location provides proper clearance of the conjunctiva and Tenon's capsule for the implant flange (long axis of implant flange = 4.6 mm). - A peritomy size of at least 6 mm by 6 mm facilitates implant placement away from radial relaxing incision. - Appropriate peritomy size is vital for ease of subsequent surgery. | Figure 12 Conjunctival peritomy with blue dot representing selected implant location
- Only one radial incision is recommended, to avoid excessive conjunctival suturing and longer healing process.
- Careful incision creation is key to maintain integrity of conjunctiva and Tenon's capsule. Careful and generous undermining is key to minimize mechanical tension and adequate coverage of the implant while closing the conjunctiva and Tenon's capsule.
- Maintain hemostasis around the scleral incision throughout the surgery to facilitate the identification and management of incisional bleeding, to avoid post-operative vitreous hemorrhage.

Syringe Preparation and Initial Implant Fill

Using aseptic technique, the implant will be filled with 0.02 mL of ranibizumab prior to insertion of the implant into the patient's eye.

1. Transfer dose from vial to syringe Caution Use the filter needle to withdraw ranibizumab from the vial. Do not use the initial fill needle for this step.; - Prepare ranibizumab vial by removing the flip-off cap and disinfecting the rubber vial septum with alcohol. - Attach a filter needle to the syringe by screwing it tightly onto the Luer lock (Figure 13). - Carefully remove the needle cap by pulling it straight off. - Using aseptic technique, withdraw all of the contents of the ranibizumab vial through the filter needle into the syringe. | Figure 13 Filter needle attached to syringe and cap removal
2. Remove air from syringe; - With the filter needle attached, hold the syringe with the needle pointing up. - If there are any air bubbles, gently tap the syringe with your finger until the bubbles rise to the top (Figure 14). - Slowly push the plunger rod just until all air is expelled from the syringe and needle. - It is important to preserve as much drug as possible in order to completely fill the implant. - Remove and properly dispose of the filter needle after air is removed from syringe. | Figure 14 No air bubbles in syringe
3. Attach initial fill needle; - Attach the initial fill needle firmly onto the syringe by screwing it tightly onto the Luer lock (Figure 15). - Carefully remove the needle cap by pulling straight off.; - Do not wipe the needle at any time.; Caution Ensure that the initial fill needle is attached to the syringe. Do not use the filter needle to fill the implant. | Figure 15 Initial fill needle attached to syringe and cap removal
4. Remove any remaining air from syringe; - With the initial fill needle attached, hold the syringe with the needle pointing up. - If there are any air bubbles, gently tap the syringe with your finger until the bubbles rise to the top (Figure 16). - Slowly push the plunger rod just until all air is expelled from the syringe and needle, and a drop of drug solution is seen at the needle tip (Figure 17). - It is important to preserve as much drug as possible in order to completely fill the implant. | Figure 16 Gently tap the syringe to dislodge bubbles Figure 17 No air bubbles and a drop of drug at the needle tip
5. Inspect the syringe for air bubbles; - Inspect the syringe and the needle hub to ensure that no air bubbles are present (Figure 18). - If air bubbles are present, continue to remove air from the syringe and reinspect.; Caution Use the syringe within 15 minutes of removing all air to avoid ranibizumab drying in the needle and impeding fluid flow. Do not use the initial fill needle if the needle is clogged. | Figure 18 No air bubbles in the syringe and needle hub
6. Load syringe into the carrier Caution Do not hold or push on the plunger rod of the syringe while inserting the needle into the implant septum.; - Retrieve insertion tool carrier with pre-positioned implant from the inner tray. - Align the syringe Luer lock above the Luer lock slot in the carrier to protect the needle from being damaged. - Lower the syringe into the carrier (Figure 19). - Push the syringe forward until it stops, taking care to avoid touching the plunger rod (Figure 20). - With the syringe loaded, (Figure 21) the initial fill needle should now be penetrating the implant septum. | Figure 19 Align and lower the syringe into the carrier Figure 20 Push the syringe into the carrier Figure 21 Syringe with initial fill needle inserted through the implant septum
7. Fill implant with ranibizumab under microscope; - Under the microscope, slowly administer ranibizumab into the implant by slightly tilting the carrier upwards (Figure 22). - The implant should be filled over approximately 5 to 10 seconds, to help avoid air entrapment in the implant reservoir. - Continue filling the implant until the implant is completely full of drug solution and all air has been expelled as evidenced by a dome of drug solution formed at the tip of the implant on the release control element (Figure 23). Caution When filling the implant, fluid should only exit the implant from the release control element. If fluid is leaking from the implant at a different location, such as the side of the implant, do not use the implant. If fluid is leaking from the septum at the needle insertion site, the needle may not be fully penetrating the implant septum. Fully push the syringe forward before continuing to fill the implant. | Figure 22 Administer ranibizumab into the implant Figure 23 Dome of drug solution forms at tip of implant as viewed under magnification
8. Inspect the filled implant under the microscope; - Inspect the implant under the microscope to ensure that the implant is completely full of drug solution (Figure 24). Warning Minimize air bubbles within the implant reservoir as they may cause slower drug release. If an air bubble is present, it must be no larger than 1/3 of the widest diameter of the implant. If excess air is observed, do not use the implant. Caution No more than 30 minutes should pass between the initial fill of the implant and the insertion into the patient's eye to ensure that the release control element remains saturated with ranibizumab. If ranibizumab dries in the release control element, the implant may not release the drug properly into the vitreous after insertion. | Figure 24 Proper appearance of implant after initial filling with ranibizumab
9. Remove the syringe and guide sleeve from the carrier
- Remove the syringe and guide sleeve from the carrier by pulling back on the syringe (Figure 25). The syringe will be locked into the guide sleeve. - Properly dispose of the used syringe together with the needle and guide sleeve in a sharps disposal container or in accordance with local requirements. | Figure 25 Remove the syringe and guide sleeve from the insertion tool carrier
10. Slide the insertion tool handle into the carrier
- Slide the insertion tool handle into the guide channel of the carrier, ensuring that both components are facing upwards (Figure 26). - Push the handle forward as far as it will go into the gripper tips (Figure 27).; Caution Do not withdraw the handle and implant until the eye is ready for insertion. Contact between the implant and any surface or object – even within the sterile field – may result in the introduction of a foreign body into the vitreous. | Figure 26 Insert the handle into the insertion tool carrier Figure 27 Fully inserted handle

Implant Insertion

1. Verify hemostasis of the scleral surface

- Clear any excess blood from the scleral surface.
- Perform careful scleral wet field cauterization as needed, particularly in the area of the sclero-pars plana incision.

2. Mark incision site

- Keep sclera dry and create discrete ink marks using a light touch.
- Mark a location 4 mm from the limbus using an inked fixed width caliper (or equivalent) at the selected implant location (Figure 28).
- Mark a 3.5 mm length for scleral dissection parallel to and 4 mm posterior to the limbus using an inked fixed width caliper (or equivalent) (Figure 29).

Figure 28
4 mm posterior to the limbus
Figure 29
Fixed width caliper measurement

3. Perform scleral incision

- Using an MVR blade, create a full thickness dissection of the sclera until the pars plana is fully visible (Figure 30).
  - Ensure scleral dissection location is away from the radial conjunctival incision.
  Caution
  The final target length for the scleral incision is 3.5 mm. Keep in mind that laser may further result in enlargement of incision and limit the secureness of the fit of the implant.
  - Confirm the length of the incision by using the largest width of the 3.5 mm incision gauge (Figure 31).
  - If the incision is over 3.5 mm, as indicated by a loose fit/side to side motion of 3.5 mm gauge, place a suture through the wound opposite the relaxing incision to reduce the incision down to 3.5 mm, and bury the knot. After suturing, confirm the incision length is 3.5 mm (Figure 31).
  - If there are any areas of visible bleeding from the wound, carefully perform diathermy.

Figure 30
Stabilize the globe and perform full thickness scleral incision
Figure 31
Confirm correct length of scleral incision

4. Perform laser treatment of the pars plana

Caution
Laser treatment may result in enlargement of the incision. Laser treatment should not be used to intentionally enlarge the length of scleral incision.
Caution
Carefully apply the laser only to the choroidal tissue in the exposed pars plana. Minimize any laser application to the surrounding scleral tissue to avoid damaging tissue integrity.

- Confirm pars plana is dry before laser treatment and keep dry throughout the procedure (with surgical sponge).
  - Consider placing a surgical sponge as a wick at one end of the incision.

Figure 32
Laser treatment of the pars plana

- Using a 532 nm laser endoprobe, apply contiguous, overlapping laser spots starting at 300 mW 1000 ms along the full length of the exposed pars plana (Figure 32). Repeat until complete ablation is achieved.
  - Maintain focus of laser on exposed pars plana.
  - Keep foot pedal depressed to achieve full 1000 ms spots (expect smoke).
  - Ensure the pars plana at the corners of scleral incision is adequately treated.
  - Do not use painting strokes with the laser.
  - Do not contact the pars plana directly with laser probe.
- Repeat application of laser along the full length of the pars plana until full or partial split of the pars plana, or other visual endpoints are achieved, as indicated by:
  - Gray color change.
  - Uniform perforated appearance.
  - Domes of vitreous fluid percolating through pars plana.
- If visual endpoint is not achieved after several passes with the laser, increase laser power in 100 mW increments.
- Once laser ablation of pars plana is completed, remeasure the entire length (including corners) of the scleral incision with 3.5 mm gauge to confirm the final post-laser incision is 3.5 mm. If final incision is greater than 3.5 mm, as indicated by a loose fit/side to side motion of 3.5 mm gauge, place a suture through the wound opposite the relaxing incision to reduce incision down to 3.5 mm.

Caution

A final post-laser incision length of 3.5 mm provides a secure fit for the implant.

Do not enlarge the scleral dissection beyond 3.5 mm as a final incision length greater than 3.5 mm may result in an improperly seated implant and will require additional suturing.

5. Perform pars plana incision; - Pass a 3.2 mm slit knife perpendicularly through the center of the scleral incision to open the underlying pars plana (Figure 33 and Figure 34). - Ensure widest part of the blade passes through the incision. - Ensure adequate hemostasis. - Carefully check for any active bleeding from the pars plana incision; if active bleeding is present, address it with fine tip diathermy within the incision before proceeding.; Caution Do not enlarge the pars plana incision with lateral movements. The incision width of 3.2 mm ensures that the pars plana incision is within the laser-treated area of the pars plana and reduces the risk of vitreous hemorrhage.; - Aim to the center of the globe. - Insert blade straight in and straight out. - Avoid sideways motion. - Avoid enlargement of the incision. - Avoid the edges of the wound. | Figure 33 Pars plana incision Figure 34 Perpendicular entry of slit knife
6. Withdraw the insertion tool handle with filled implant
- Withdraw the insertion tool handle, which is now attached to the gripper tips and implant, by slowly pulling the carrier and handle apart (Figure 35). - Take care not to touch implant to any surface other than incision.; Caution When holding the insertion tool handle, take care not to touch the implant to any surface other than the sclero-pars plana incision during the insertion procedure. Do not use the implant if it is inadvertently released or is contaminated through contact with any surface other than the exposed sclera, including objects within the surgical field. | Figure 35 Withdraw the insertion tool handle with filled implant
7. Stabilize the globe; - Prior to inserting the implant, stabilize the globe with forceps to prevent unwanted eye movement (Figure 36). - The forceps should remain in place until the insertion procedure is complete. | Figure 36 Stabilize the globe with forceps
8. Orient the implant; - Orient the long axis of the implant flange with the length of the sclero-pars plana incision (Figure 37). - Aligning the implant in this direction enables the intended seating of the implant within the sclero-pars plana incision. | Figure 37 The long axis of the implant aligned with the length of the sclero-pars plana incision
9. Insert the implant Warning Perpendicular entry of the implant is important to avoid contact between the implant and intraocular structures such as the lens, as contact between the implant and the intraocular structures may cause adverse events such as traumatic cataract. Warning Avoid excessive force on the globe by first ensuring that the tip of the implant has passed through the sclero-pars plana incision before slowly pushing the implant into place.; - Slowly insert the implant through the sclero-pars plana incision perpendicular to the globe (Figure 38 and Figure 39). - A slight initial twisting motion may be helpful to ease the implant through the sclero-pars plana incision (Figure 40). - Continue pressing the implant slowly through the incision until the insertion tool handle gripper tips abut the sclera. - Per the surgeon's discretion, the infusion line may be turned on while inserting the implant. - If excess vitreous prolapses from the incision, use the vitrector to remove it and then place the implant. - If a small amount of vitreous prolapse is present, place the implant first and then use the vitrector to remove the excess. Only use the vitrector to remove vitreous prolapse (do not use surgical sponge and/or scissors). | Figure 38 Perpendicular entry of the implant Figure 39 Implant insertion Figure 40 Implant insertion with a slight initial twisting motion
10. Release the implant; - Ensure that the long axis of the implant is properly aligned with the sclero-pars plana incision before releasing the implant from the insertion tool. - The forceps that are stabilizing the globe should remain in place. - Release the implant by depressing the release button completely (Figure 41 and Figure 42).; Caution If the implant flange is not parallel to the limbus after releasing, it needs to be repositioned solely using the gripper tips of the insertion tool handle. Reposition gently to avoid damage to the implant and to avoid contact between the implant and intraocular structures such as the lens. Avoid excessive manipulation of the implant flange. Do not use any other rigid instruments to reposition. | Figure 41 Release implant with the release button Figure 42 Implant release
11. Seat the implant Caution Use the insertion tool gripper tips to seat the implant. Do not use any other rigid instruments as they may damage the implant. Caution Ensure that the long axis of the implant is aligned with the length of the sclero-pars plana incision and that the implant is seated flush against the sclera.; - Remove finger from the release button to close the insertion tool gripper tips. - Gently press the closed gripper tips against the center of the implant to seat the implant flush against the sclera (Figure 43). - Clean any residual vitreous around the implant flange using a vitrector. | Figure 43 Seat the implant
12. Suture Tenon's capsule and conjunctiva; - Close both Tenon's capsule and conjunctiva, with Vicryl or gut sutures, ensuring complete coverage of the implant flange. - Use scleral anchoring at the apex of the peritomy. - Ensure suture placement away from the implant (Figure 44).; Caution Do not place a suture directly over the implant, otherwise adverse events including incomplete healing, infection, and discomfort can occur. Caution Complete closure of both Tenon's capsule and conjunctiva across the surgical site is critical to minimize potential complications such as conjunctival retraction over the implant. | Figure 44 Suture conjunctiva

13. Remove infusion cannula

- If the infusion was previously turned on, then set the infusion pressure to 20 mmHg before removing the infusion cannula.
- Check for persistent leaks at the infusion cannula site and suture if necessary.

14. Check Intraocular Pressure (IOP)

- Using digital palpation, check the IOP. If necessary, inject additional fluid to restore IOP.

15. Check implant placement

- Perform indirect ophthalmoscopy to confirm implant position and to examine for the presence of any complications.

Disposal and Post-insertion Procedures

1. Dispose of used Susvimo components and tools

- Do not recap the needle or detach it from the syringe. Dispose of the used Susvimo components and tools in a sharps disposal container or in accordance with local requirements.

2. Perform post-insertion procedures

- Post-insertion procedures are consistent with standard post-surgical procedures.

3. Post-insertion patient instructions

Provide the patient with the following post-operative instructions:

- Positioning:
  - Keep head above shoulder level for the rest of the day.
  - Sleep with head elevated on 3 or more pillows if lying down during the day and night after implant insertion.
- Information on caring for the eye after the procedure, including but not limited to the following:
  - Do not remove the eye shield until they are instructed to do so by their physician. At bedtime, continue to wear the eye shield for at least 7 nights following implant insertion.
  - Administer all post-operative eye medications, as directed by their physician.
  - Do not push on the eye, rub the eye, or touch the region of the eye where the implant is located (underneath the eyelid in the upper and outer part of the eye) for 30 days following implant insertion. Avoid rubbing the eye or touching the area where the implant is located as much as possible at all other times but if necessary to do so, make sure hands are cleaned prior to touching the eye.
  - Do not participate in strenuous activities until 1 month after implant insertion or after discussion with their physician.
- Monitor for symptoms that may require immediate medical attention while the implant is in place.
- MR Conditional information:
  - The surgeon should inform the patient that the implant is MR Conditional (as noted on their Susvimo implant card) and if patient needs to undergo an MRI, they should let their doctor know they have Susvimo implanted in their eye.
  - After implant insertion, the surgeon should give the patient the implant card with the appropriate information filled in, and should advise the patient to keep the card in a safe place, e.g. his or her wallet, for future reference. The surgeon should advise the patient that this implant card contains important information related to the Susvimo implant and that the card should be shown to their current and future health care providers.

Explanation of symbols on product or package labeling

Table 6 Symbols on blister tray and carton
Symbol | Title
 | Manufacturer
 | Prescription only
 | Do not re-use
 | Do not use if package is damaged
 | Consult Instructions for Use
 | Sterilized by irradiation
 | Sterilized using ethylene oxide
 | Temperature limit
 | Expiration date/Use by date
 | Lot/Batch number
 | MR Conditional

Manufactured by:

Genentech, Inc.
A Member of the Roche Group
1 DNA Way
South San Francisco, CA 94080-4990
U.S. License No.: 1048

SUSVIMO is a registered trademark of Genentech, Inc.
©2025 Genentech, Inc. All rights reserved.

This Instructions for Use has been approved by the U.S. Food and Drug Administration.
Approved: 9/2025

INSTRUCTIONS FOR USE

Susvimo™
(ranibizumab injection)
For Susvimo ocular implant use
Instructions for Use

Implant Removal Procedure

Caution: Federal Law (USA) restricts this device to sale by or on the order of a physician.

Susvimo procedures should be performed by an ophthalmologist experienced in vitreoretinal surgery.

Refer to the Susvimo (ranibizumab injection) 100 mg/mL prescribing information for a complete list of indications, contraindications, warnings, precautions, and adverse events.

Contents

Introduction

3 | Device Description
3 | Components
4 | Intended Use/ Indications for Use
4 | Warnings
4 | Precautions
5 | How Supplied, Handling, and Storage

Instructions for Use

6 | Introduction and Materials
7 | Preparatory Procedures
8 | Implant Removal
16 | Disposal and Post-removal Procedures
17 | Explanation of symbols on product or package labeling

Introduction

These instructions include only the implant removal procedure for the Susvimo implant. Refer to the Susvimo Instructions for Use for the initial fill and implant procedure and prescribing information for the refill-exchange procedure.

Device Description

Susvimo is an intraocular drug delivery system designed to be used specifically with Susvimo (ranibizumab injection) 100 mg/mL.

These Instructions for Use describe the required materials and steps necessary for removal of the Susvimo implant.

Components

Figure 1
Susvimo components for implant removal procedure

Susvimo explant tool

Susvimo explant tool (Figure 2) is a pair of forceps with contoured tips, which are designed to grasp underneath the implant flange to securely engage the implant during removal.

Figure 2
Susvimo explant tool

Intended Use/ Indications for Use

Susvimo explant tool is approved for use with Susvimo ocular implant. Refer to the Susvimo (ranibizumab injection) prescribing information for a complete list of indications, contraindications, warnings, precautions, and adverse events.

Warnings

- Do not use if the sterility has been compromised or the contents have been dropped, damaged or tampered with.
- Do not grasp the implant by the short axis of the implant flange. Remove the implant in a gentle manner. Perpendicular exit of the implant is important to avoid contact between the implant and intraocular structures such as the lens.

Precautions

- Read and follow all instructions, warnings, and cautions prior to use.
- Susvimo procedures should be performed by an ophthalmologist experienced in vitreoretinal surgery.
- Use Susvimo components and materials as specified in these instructions to perform the implant removal procedure.

How Supplied, Handling, and Storage

- Susvimo explant tool has been electron beam sterilized. Do not reprocess or resterilize.
- Susvimo explant tool is for single-use only. Do not reuse the Susvimo explant tool.
- Do not open sealed tray until time of use.
- Do not use if the package is damaged or broken as sterility may be compromised.
- Do not use past the expiration date printed on the label.
- Susvimo explant tool should be stored at a room temperature 15°C to 25°C (59°F to 77°F).

Instructions for Use

Introduction and Materials

Removal of the Susvimo implant requires a surgical procedure that is performed in an operating room.

Materials List

Materials that are required and provided for the procedure are listed in Table 1.

Table 1 Susvimo sterile components that are provided for implant removal

Item Description

Susvimo explant tool

Materials required but not provided are listed in Table 2.

Table 2 Additional materials required but not provided for implant removal

Item Description

Surgical microscope

Vitrectomy surgical control system

Standard 25 G or 27 G vitrectomy set up

Standard vitrectomy tray (including 0.12 straight toothed forceps and blunt wescott scissors)

Cauterization equipment (including standard fine tip diathermy and eraser tip wet-field cautery)

Ophthalmic broad-spectrum microbicide solution

Surgical scalpel blade #15

Non-absorbable sutures for sclera (suggested Nylon)

Gut or Vicryl sutures for conjunctival tissues (suggested 7-0 to 9-0: monofilament recommended)

Indirect ophthalmoscope and lens

Drapes

Preparatory Procedures

1. Inspect and open sterile packaging

- Prior to use in the operating room, inspect the sterile packaging of the explant tool for damage.
- Check the expiration date printed on the label.
- Open sterile packaging and using aseptic technique, remove the explant tool from the tray.
- Inspect the explant tool and place onto sterile surface.

Warning

Do not use if the sterility has been compromised or the contents have been dropped, damaged, or tampered with.

2. Patient Preparation

- Dilate the pupil of the eye.
- Place the patient in a supine position on the operating table.
- Implant removal is a surgical procedure and therefore requires sterile controls (i.e. use of ophthalmic broad-spectrum microbicide solution on eye including lids and lashes and draping) be in place to minimize the risk of ocular infection.
- Perform the procedure under local anesthesia using either peribulbar, retrobulbar, or sub-Tenon's technique.
- Place lid speculum.

Implant Removal

Perform the implant removal procedure under the microscope. Consider placing a traction suture for better visualization of the superotemporal quadrant throughout the entire implant removal procedure.

1. Place infusion line

- Place an infusion cannula in the inferotemporal quadrant via an angled entry wound.
- Attach the infusion line, however keep the infusion off.

2. Perform conjunctival peritomy

- Create at least a 6 mm by 6 mm peritomy of the conjunctiva and Tenon's capsule around the implant flange (Figure 3).

Figure 3
Conjunctival peritomy

3. Remove fibrous capsule covering implant

- Remove any fibrous capsule or scar tissue that may have formed over the implant flange and septum (Figure 4 and Figure 5).
  - To expose the implant, use a scalpel to make an incision in the tissue around the entire circumference of the implant (Figure 4).
  - Use forceps to carefully dissect the implant flange and neck from the surrounding tissue so that the edges of the flange are completely exposed and the implant is free of any adherent tissue (Figure 5).

Figure 4
Incision to remove tissue that may be covering the implant flange and septum

Figure 5
Exposed implant

4. Stabilize the globe and align the explant tool

- Stabilize the globe with forceps to prevent unwanted eye movement.
- With the explant tool oriented perpendicular to the globe, align the contoured tips with the long axis of the implant flange (Figure 6).

Figure 6
Align the explant tool along the long axis of the implant flange

5. Grasp the implant

Warning

Do not grasp the implant by the short axis of the implant flange. Remove the implant in a gentle manner. Perpendicular exit of the implant is important to avoid contact between the implant and intraocular structures such as the lens.

- Use the contoured tips of the explant tool to gently grasp underneath the long axis of the implant flange (Figure 7).

Figure 7
Grasp underneath the long axis of the implant flange

6. Remove the implant

- Once the implant is secured in the explant tool, in a gentle manner pull the implant from the eye in a perpendicular motion to avoid contact with adjacent intraocular structures.
- During removal, use forceps to stabilize the globe and provide counter traction to help release the surrounding tissue (Figure 8).
- During removal, continue to maintain perpendicular orientation of the implant relative to the globe (Figure 9).
  Figure 8
  Implant removal
  Figure 9
  Perpendicular exit of the implant
- If needed per the surgeon's discretion, the infusion line on the vitrectomy surgical system can be turned on during implant removal.
- Control any scleral or conjunctival bleeding, using cauterization if needed, and clear any vitreous prolapse present within or around the scleral wound using a vitrectomy setup.
  Figure 10
  Appearance of the scleral wound after implant removal

7. Suture the sclera

- Completely close the scleral incision with non-absorbable (suggested Nylon) sutures (Figure 11). More than one suture will be needed to close the wound. It is recommended to place equally spaced partial thickness interrupted sutures.
- Ensure that the knots are buried.

Caution

Do not overtighten the scleral sutures, to minimize excessive tensions on the sclera or cornea.

Figure 11
Suture scleral wound using multiple sutures

8. Suture conjunctiva

- Close Tenon's capsule and conjunctiva to completely cover the scleral incision (Figure 12).

Caution

Completely close Tenon's capsule and conjunctiva to minimize potential post-removal complications.

Figure 12
Suture conjunctiva post-removal

9. Remove infusion cannula

- If the infusion was previously turned on, then set the infusion pressure to 20 mmHg before removing the infusion cannula.
- Place suture at infusion cannula site as needed.

10. Check Intraocular Pressure (IOP) using digital palpation

11. Perform indirect ophthalmoscopy to examine for the presence of any complications

Disposal and Post-removal Procedures

1. Dispose of the used components

- Dispose of the used explant tool together with the implant in a biohazard waste container or in accordance with local requirements.

2. Perform post-removal procedures

- Post-removal procedures are consistent with standard post-surgical procedures.

3. Post-removal patient instructions

- Provide the patient with the following post-operative instructions:
  - Positioning:
    - Keep head above shoulder level for the rest of the day.
    - Sleep with head elevated on 3 or more pillows if lying down during the day and night after implant removal.
  - Information on caring for the eye after the procedure, including but not limited to:
    - Monitor for symptoms that may require immediate attention.
    - Wear an eye shield at bedtime for at least 7 nights.
    - Do not participate in strenuous activities until 14 days following the implant removal procedure.
    - Administer all post-operative anti-inflammatory and antimicrobial drops, as directed by their physician.

Explanation of symbols on product or package labeling

Table 3 Symbols on blister tray and carton
Symbol | Title
 | Manufacturer
 | Prescription only
 | Do not re-use
 | Do not use if package is damaged
 | Consult Instructions for Use
 | Sterilized by irradiation
 | Temperature limit
 | Expiration date/ Use by date
 | Lot/Batch number

Manufactured by:
Genentech, Inc.
A Member of the Roche Group
1 DNA Way
South San Francisco, CA 94080-4990

U.S. License No.: 1048

SUSVIMO is a trademark of Genentech, Inc.
©2021 Genentech, Inc.
All rights reserved.

This Instructions for Use has been approved by the U.S. Food and Drug Administration.

Approved: 10/2021

Representative sample of labeling (see the HOW SUPPLIED section for complete listing):

PRINCIPAL DISPLAY PANEL - Kit Carton

NDC 50242-078-55

Susvimo™
(ranibizumab injection)

See instructions for use
included with the
Susvimo ocular implant
with insertion tool assembly

100 mg/mL

Vial contains 10 mg/0.1 mL ranibizumab

For use with Susvimo ocular implant

Dispense the enclosed Medication Guide to each patient.

Carton contents:

- One Susvimo single-dose vial
- One Susvimo initial fill needle

Rx only

Genentech

10233586

PRINCIPAL DISPLAY PANEL - 100 mg/mL Vial Carton

NDC 50242-078-12

Susvimo®
(ranibizumab injection)

100 mg/mL

Vial contains
10 mg/0.1 mL ranibizumab

For use with Susvimo
ocular implant

Dispense the enclosed
Medication Guide to each patient.

Rx only

1 Single-dose vial

Genentech

11032207